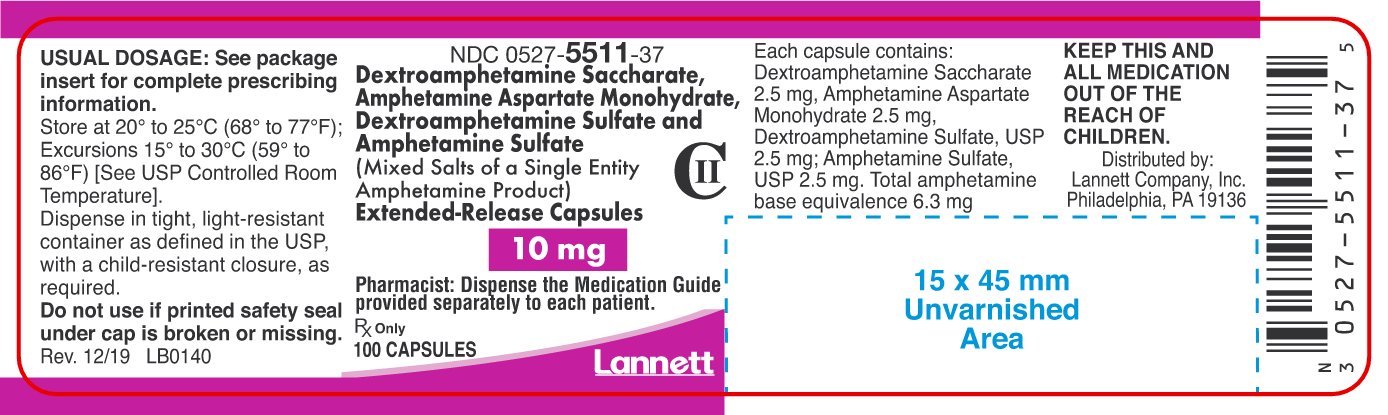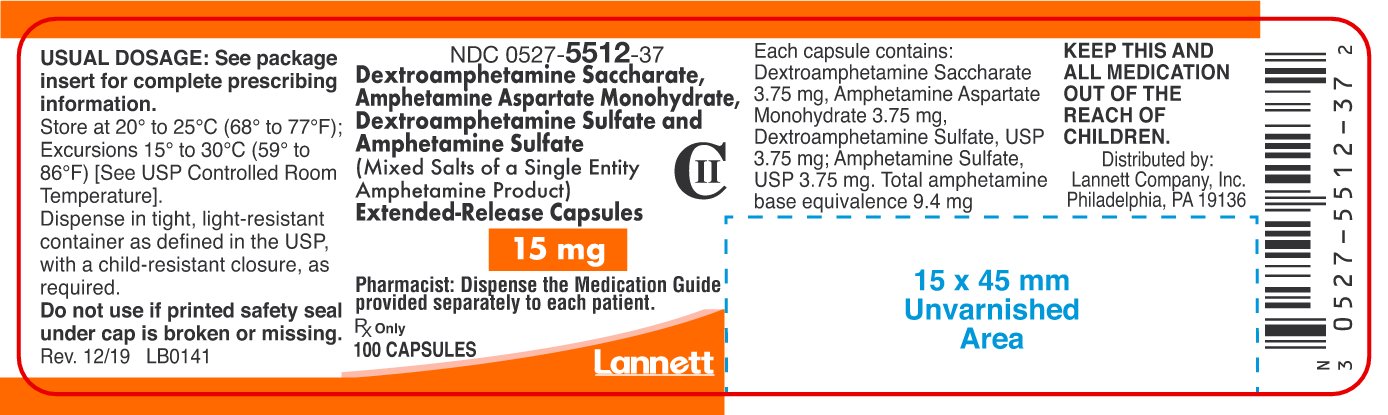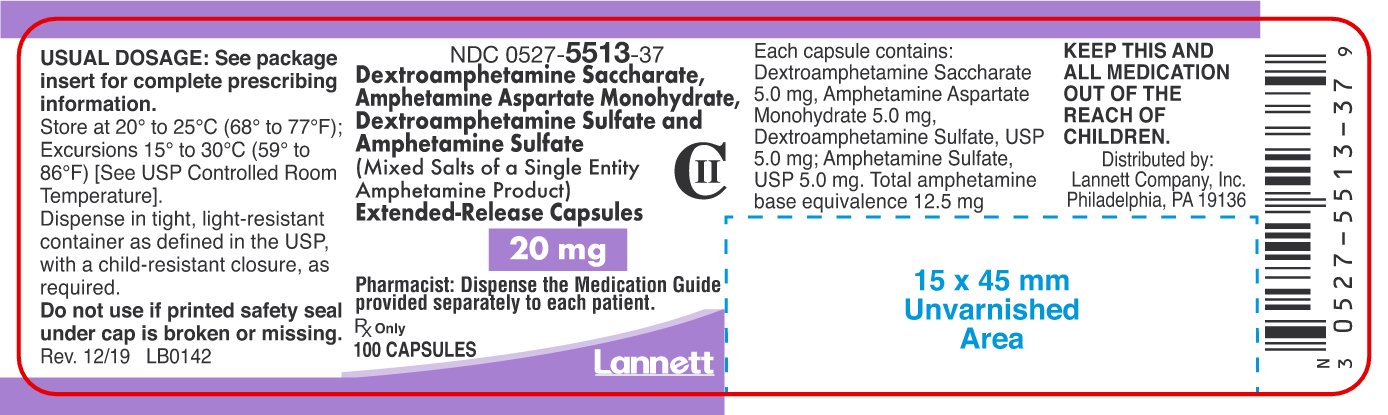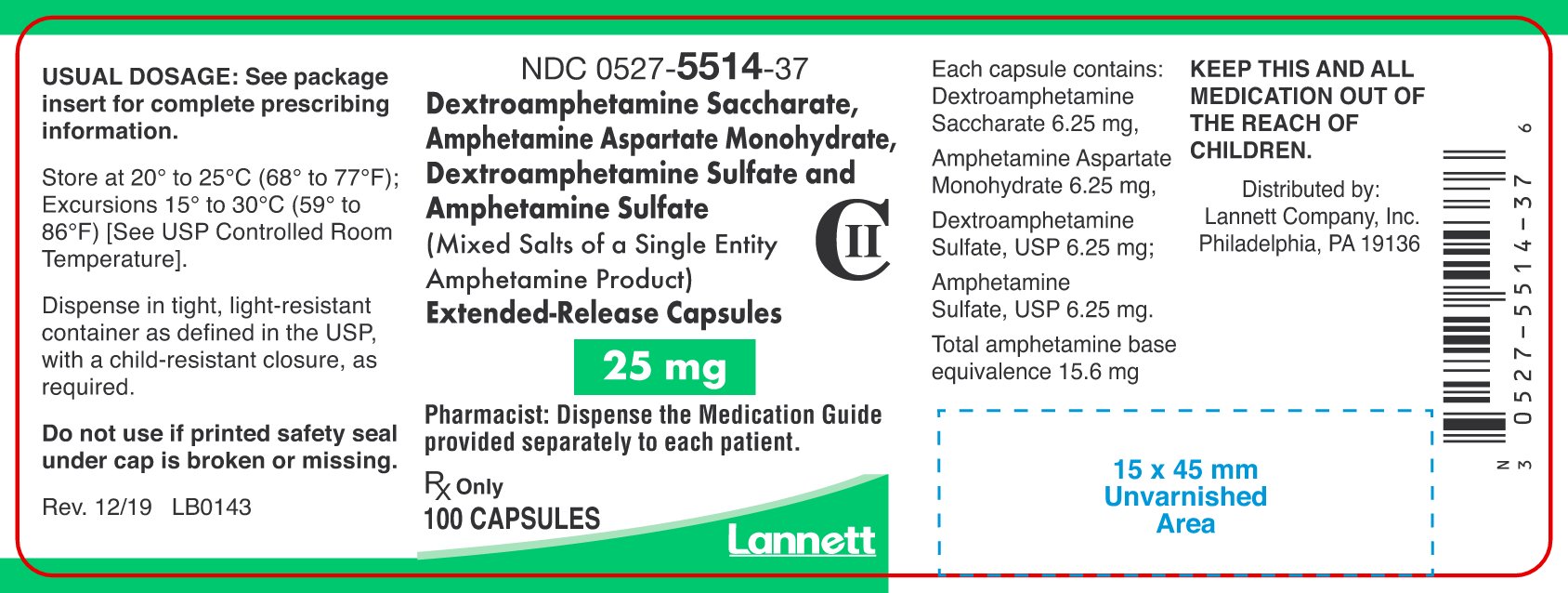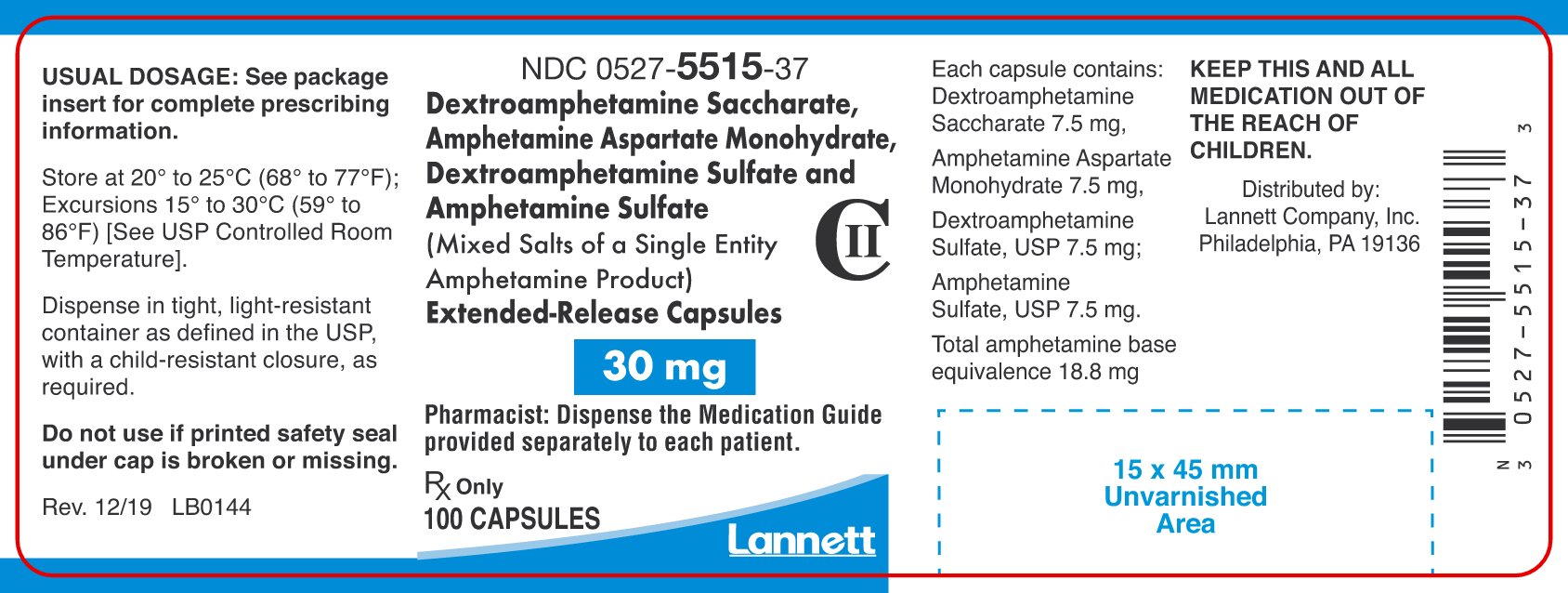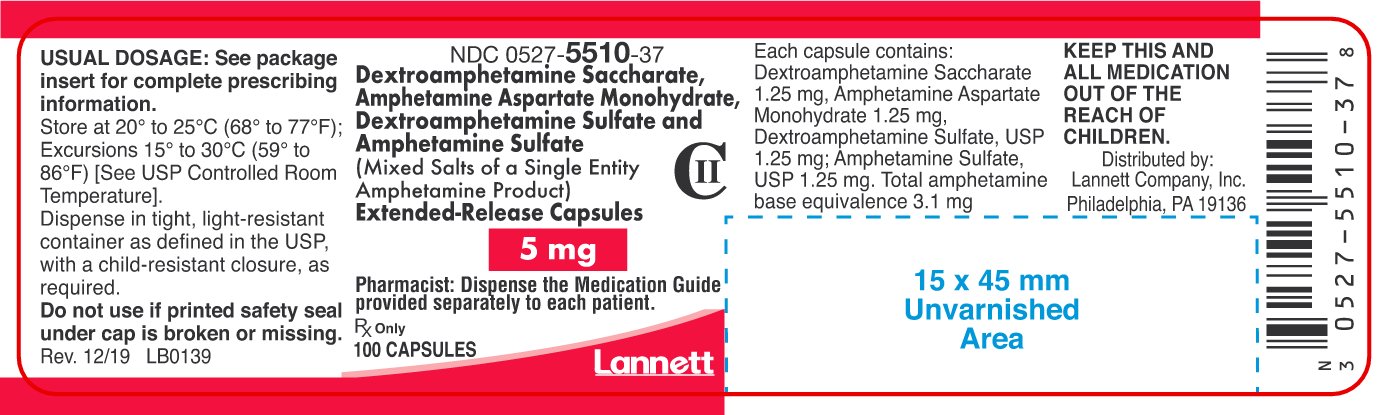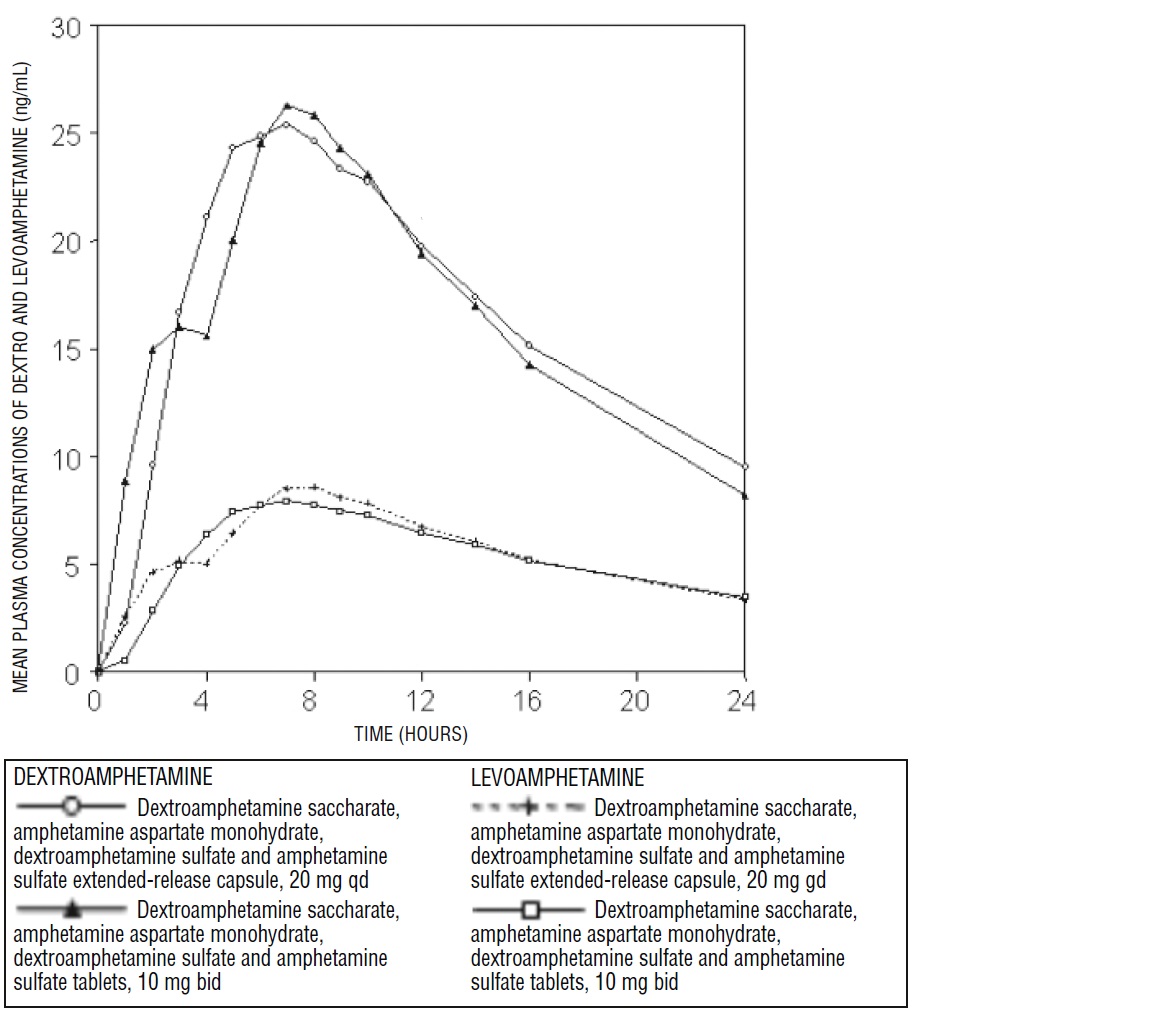 DRUG LABEL: Dextroamphetamine Saccharate, Amphetamine Aspartate Monohydrate, Dextroamphetamine Sulfate, and Amphetamine Sulfate
NDC: 0527-5510 | Form: CAPSULE, EXTENDED RELEASE
Manufacturer: Lannett Company, Inc.
Category: prescription | Type: HUMAN PRESCRIPTION DRUG LABEL
Date: 20251212
DEA Schedule: CII

ACTIVE INGREDIENTS: DEXTROAMPHETAMINE SACCHARATE 1.25 mg/1 1; DEXTROAMPHETAMINE SULFATE 1.25 mg/1 1; AMPHETAMINE ASPARTATE MONOHYDRATE 1.25 mg/1 1; AMPHETAMINE SULFATE 1.25 mg/1 1
INACTIVE INGREDIENTS: Gelatin, Unspecified; HYPROMELLOSE 2910 (50 MPA.S); Methacrylic Acid And Ethyl Acrylate Copolymer; FERRIC OXIDE RED; FERRIC OXIDE YELLOW; HYPROMELLOSE 2910 (3 MPA.S); HYPROMELLOSE 2910 (6 MPA.S); POLYETHYLENE GLYCOL 400; POLYSORBATE 80; TITANIUM DIOXIDE; SUCROSE; TALC; TRIETHYL CITRATE; D&C YELLOW NO. 10; FD&C BLUE NO. 1; FD&C YELLOW NO. 6; Fd&C Red No. 40; Propylene Glycol; Shellac; Fd&C Blue No. 1 Aluminum Lake

HIGHLIGHTS OF PRESCRIBING INFORMATION

These highlights do not include all the information needed to use DEXTROAMPHETAMINE SACCHARATE, AMPHETAMINE ASPARTATE MONOHYDRATE, DEXTROAMPHETAMINE SULFATE, and AMPHETAMINE SULFATE (Mixed Salts of a Single-Entity Amphetamine Product) EXTENDED-RELEASE CAPSULES safely and effectively. See full prescribing information for DEXTROAMPHETAMINE SACCHARATE, AMPHETAMINE ASPARTATE MONOHYDRATE, DEXTROAMPHETAMINE SULFATE, and AMPHETAMINE SULFATE (Mixed Salts of a Single-Entity Amphetamine Product) EXTENDED-RELEASE CAPSULES.
DEXTROAMPHETAMINE SACCHARATE, AMPHETAMINE ASPARTATE MONOHYDRATE, DEXTROAMPHETAMINE SULFATE, and AMPHETAMINE SULFATE extended-release capsules, for oral use, CII
Initial U.S. Approval: 2001

RECENT MAJOR CHANGES

Boxed Warning | 7/2019
Dosage and Administration (2.1) | 7/2019
Warnings and Precautions (5.1) | 7/2019

WARNING: ABUSE AND DEPENDENCE

See full prescribing information for complete boxed warning

- CNS stimulants, including dextroamphetamine saccharate, amphetamine aspartate monohydrate, dextroamphetamine sulfate and amphetamine sulfate extended-release capsules, other amphetamine-containing products, and methylphenidate, have a high potential for abuse and dependence (5.1, 9.3).
- Assess the risk of abuse prior to prescribing and monitor for signs of abuse and dependence while on therapy (9.2, 9.3).

1 INDICATIONS AND USAGE

Dextroamphetamine saccharate, amphetamine aspartate monohydrate, dextroamphetamine sulfate and amphetamine sulfate extended-release capsules, a CNS stimulant, is indicated for the treatment of attention deficit hyperactivity disorder (ADHD). (1)

- Children (ages 6-12): Efficacy was established in one 3-week outpatient, controlled trial and one analogue classroom, controlled trial in children with ADHD. (14)
- Adolescents (ages 13-17): Efficacy was established in one 4-week controlled trial in adolescents with ADHD. (14)
- Adults: Efficacy was established in one 4-week controlled trial in adults with ADHD. (14)

2 DOSAGE AND ADMINISTRATION

- Pediatric patients (ages 6-17): 10 mg once daily in the morning. Maximum dose for children 6-12 years of age is 30 mg once daily. (2.2, 2.3, 2.4)
- Adults: 20 mg once daily in the morning. (2.5)
- Pediatric patients (ages 6-17) with severe renal impairment: 5 mg once daily in the morning. Maximum dose for children 6-12 years of age with severe renal impairment is 20 mg once daily. (2.6, 8.6)
- Adults with severe renal impairment: 15 mg once daily in the morning. (2.6, 8.6)
- Patients with ESRD: not recommended. (2.6, 8.6)

3 DOSAGE FORMS AND STRENGTHS

Extended release capsules: 5 mg, 10 mg, 15 mg, 20 mg, 25 mg, 30 mg (3)

4 CONTRAINDICATIONS

- Advanced arteriosclerosis (4)
- Symptomatic cardiovascular disease (4)
- Moderate to severe hypertension (4)
- Hyperthyroidism (4)
- Known hypersensitivity or idiosyncrasy to amphetamine (4)
- Glaucoma (4)
- Agitated states (4)
- History of drug abuse (4)
- During or within 14 days following the administration of monoamine oxidase inhibitors (MAOI) (4, 7.1)

5 WARNINGS AND PRECAUTIONS

- Serious Cardiovascular Reactions: Sudden death has been reported with usual doses of CNS stimulants in children and adolescents with structural cardiac abnormalities or other serious heart problems; sudden death, stroke, and myocardial infarction have been reported in adults taking CNS stimulants at usual doses. Stimulant drugs should not be used in patients with known structural cardiac abnormalities, cardiomyopathy, serious heart rhythm abnormalities, coronary artery disease, or other serious heart problems. (5.2)
- Increase in Blood Pressure: Monitor blood pressure and pulse at appropriate intervals. Use with caution in patients for whom blood pressure increases may be problematic. (5.2)
- Psychiatric Adverse Events: Stimulants may cause treatment-emergent psychotic or manic symptoms in patients with no prior history, or exacerbation of symptoms in patients with pre-existing psychosis. Evaluate for bipolar disorder prior to stimulant use. Monitor for aggressive behavior. (5.3)
- Long-Term Suppression of Growth: Monitor height and weight at appropriate intervals. (5.4)
- Seizures: May lower the convulsive threshold. Discontinue in the presence of seizures. (5.5)
- Peripheral Vasculopathy, including Raynaud's phenomenon: Stimulants used to treat ADHD are associated with peripheral vasculopathy, including Raynaud's phenomenon. Careful observation for digital changes is necessary during treatment with ADHD stimulants. (5.6)
- Serotonin Syndrome: Increased risk when co-administered with serotonergic agents (e.g., SSRIs, SNRIs, triptans), but also during overdosage situations. If it occurs, discontinue dextroamphetamine saccharate, amphetamine aspartate monohydrate, dextroamphetamine sulfate and amphetamine sulfate extended-release capsules and initiate supportive treatment (4, 5.7, 10).
- Visual Disturbance: Difficulties with accommodation and blurring of vision have been reported with stimulant treatment. (5.8)
- Tics: May exacerbate tics. Evaluate for tics and Tourette's syndrome prior to stimulant administration. (5.9)

6 ADVERSE REACTIONS

- Children (ages 6 to 12): Most common adverse reactions (≥5% and with a higher incidence than on placebo) were loss of appetite, insomnia, abdominal pain, emotional lability, vomiting, nervousness, nausea, and fever. (6.1)
- Adolescents (ages 13 to 17): Most common adverse reactions (≥5% and with a higher incidence than on placebo) were loss of appetite, insomnia, abdominal pain, weight loss, and nervousness. (6.1)
- Adults: Most common adverse reactions ≥5% and with a higher incidence than on placebo were dry mouth, loss of appetite, insomnia, headache, weight loss, nausea, anxiety, agitation, dizziness, tachycardia, diarrhea, asthenia, and urinary tract infections. (6.1)

To report SUSPECTED ADVERSE REACTIONS, contact Lannett Company, Inc. at 1-844-834-0530 or FDA at 1-800-FDA-1088 or www.fda.gov/medwatch

7 DRUG INTERACTIONS

- MAOI antidepressants are contraindicated; MAOIs potentiate the effects of amphetamine. Do not administer dextroamphetamine saccharate, amphetamine aspartate monohydrate, dextroamphetamine sulfate and amphetamine sulfate extended-release capsules during or within 14 days after use of MAOI. (4, 7.1)
- Alkalinizing agents (GI antacids and urinary): These agents increase blood levels of amphetamine. (7.1)
- Acidifying agents (GI and urinary): These agents reduce blood levels of amphetamine. (7.1)
- Adrenergic blockers, antihistamines, antihypertensives, phenobarbital, phenytoin, veratrum alkaloids, and ethosuximide: Effects may be reduced by amphetamines. (7.1)
- Tricyclic antidepressants, norepinephrine, and meperidine: Effects may be potentiated by amphetamines. (7.1)

8 USE IN SPECIFIC POPULATIONS

- Pregnancy: May cause fetal harm. (8.1)
- Lactation: Breastfeeding not recommended. (8.2)

FULL PRESCRIBING INFORMATION

WARNING: ABUSE AND DEPENDENCE

CNS stimulants, including dextroamphetamine saccharate, amphetamine aspartate monohydrate, dextroamphetamine sulfate and amphetamine sulfate extended-release capsules, other amphetamine-containing products, and methylphenidate, have a high potential for abuse and dependence. Assess the risk of abuse prior to prescribing and monitor for signs of abuse and dependence while on therapy [see Warnings and Precautions (5.1) and Drug Abuse and Dependence (9.2, 9.3)].

1 INDICATIONS AND USAGE

1.1 Attention Deficit Hyperactivity Disorder

Dextroamphetamine saccharate, amphetamine aspartate monohydrate, dextroamphetamine sulfate and amphetamine sulfate extended-release capsules are indicated for the treatment of attention deficit hyperactivity disorder (ADHD).

The efficacy of dextroamphetamine saccharate, amphetamine aspartate monohydrate, dextroamphetamine sulfate and amphetamine sulfate extended-release capsules in the treatment of ADHD was established on the basis of two controlled trials in children aged 6 to 12, one controlled trial in adolescents aged 13 to 17, and one controlled trial in adults who met DSM-IV® criteria for ADHD [ see Clinical Studies (14) ].

A diagnosis of ADHD (DSM-IV®) implies the presence of hyperactive-impulsive or inattentive symptoms that caused impairment and were present before age 7 years. The symptoms must cause clinically significant impairment, e.g., in social, academic, or occupational functioning, and be present in two or more settings, e.g., school (or work) and at home. The symptoms must not be better accounted for by another mental disorder. For the Inattentive Type, at least six of the following symptoms must have persisted for at least 6 months: lack of attention to details/careless mistakes; lack of sustained attention; poor listener; failure to follow through on tasks; poor organization; avoids tasks requiring sustained mental effort; loses things; easily distracted; forgetful. For the Hyperactive-Impulsive Type, at least six of the following symptoms must have persisted for at least 6 month: fidgeting/squirming; leaving seat; inappropriate running/climbing; difficulty with quiet activities; "on the go;" excessive talking; blurting answers; can't wait turn; intrusive. The Combined Type requires both inattentive and hyperactive-impulsive criteria to be met.

Special Diagnostic Considerations

Specific etiology of this syndrome is unknown, and there is no single diagnostic test. Adequate diagnosis requires the use not only of medical but of special psychological, educational, and social resources. Learning may or may not be impaired. The diagnosis must be based upon a complete history and evaluation of the patient and not solely on the presence of the required number of DSM-IV® characteristics.

Need for Comprehensive Treatment Program

Dextroamphetamine saccharate, amphetamine aspartate monohydrate, dextroamphetamine sulfate and amphetamine sulfate extended-release capsules are indicated as an integral part of a total treatment program for ADHD that may include other measures (psychological, educational, social) for patients with this syndrome. Drug treatment may not be indicated for all patients with this syndrome. Stimulants are not intended for use in the patient who exhibits symptoms secondary to environmental factors and/or other primary psychiatric disorders, including psychosis. Appropriate educational placement is essential and psychosocial intervention is often helpful. When remedial measures alone are insufficient, the decision to prescribe stimulant medication will depend upon the physician's assessment of the chronicity and severity of the child's symptoms.

Long-Term Use

The effectiveness of dextroamphetamine saccharate, amphetamine aspartate monohydrate, dextroamphetamine sulfate and amphetamine sulfate extended-release capsules for long-term use, i.e., for more than 3 weeks in children and 4 weeks in adolescents and adults, has not been systematically evaluated in controlled trials. Therefore, the physician who elects to use dextroamphetamine saccharate, amphetamine aspartate monohydrate, dextroamphetamine sulfate and amphetamine sulfate extended-release capsules for extended periods should periodically re-evaluate the long-term usefulness of the drug for the individual patient.

2 DOSAGE AND ADMINISTRATION

2.1 Important Information Prior to Initiating Treatment

Prior to initiating treatment with dextroamphetamine saccharate, amphetamine aspartate monohydrate, dextroamphetamine sulfate and amphetamine sulfate extended-release capsules, assess for the presence of cardiac disease (e.g., perform a careful history, family history of sudden death or ventricular arrhythmia, and physical exam) [see Warnings and Precautions (5.2)].

Assess the risk of abuse prior to prescribing and monitor for signs of abuse and dependence while on therapy. Maintain careful prescription records, educate patients about abuse, monitor for signs for abuse and overdose, and periodically re-evaluate the need for dextroamphetamine saccharate, amphetamine aspartate monohydrate, dextroamphetamine sulfate and amphetamine sulfate extended-release capsules use [see Warnings and Precautions (5.1), Drug Abuse and Dependence (9)].

2.2 Dosing Considerations for All Patients

Individualize the dosage according to the therapeutic needs and response of the patient. Administer dextroamphetamine saccharate, amphetamine aspartate monohydrate, dextroamphetamine sulfate and amphetamine sulfate extended-release capsules at the lowest effective dosage.

Based on bioequivalence data, patients taking divided doses of immediate-release dextroamphetamine saccharate, amphetamine aspartate monohydrate, dextroamphetamine sulfate and amphetamine sulfate, (for example, twice daily), may be switched to dextroamphetamine saccharate, amphetamine aspartate monohydrate, dextroamphetamine sulfate and amphetamine sulfate extended-release capsules at the same total daily dose taken once daily. Titrate at weekly intervals to appropriate efficacy and tolerability as indicated.

Dextroamphetamine saccharate, amphetamine aspartate monohydrate, dextroamphetamine sulfate and amphetamine sulfate extended-release capsules may be taken whole, or the capsule may be opened and the entire contents sprinkled on applesauce. If the patient is using the sprinkle administration method, the sprinkled applesauce should be consumed immediately; it should not be stored. Patients should take the applesauce with sprinkled beads in its entirety without chewing. The dose of a single capsule should not be divided. The contents of the entire capsule should be taken, and patients should not take anything less than one capsule per day.

Dextroamphetamine saccharate, amphetamine aspartate monohydrate, dextroamphetamine sulfate and amphetamine sulfate extended-release capsules may be taken with or without food.

Dextroamphetamine saccharate, amphetamine aspartate monohydrate, dextroamphetamine sulfate and amphetamine sulfate extended-release capsules should be given upon awakening. Afternoon doses should be avoided because of the potential for insomnia.

Where possible, dextroamphetamine saccharate, amphetamine aspartate monohydrate, dextroamphetamine sulfate and amphetamine sulfate extended-release capsules therapy should be interrupted occasionally to determine if there is a recurrence of behavioral symptoms sufficient to require continued therapy.

2.3 Children

In children with ADHD who are 6-12 years of age and are either starting treatment for the first time or switching from another medication, start with 10 mg once daily in the morning; daily dosage may be adjusted in increments of 5 mg or 10 mg at weekly intervals. When in the judgment of the clinician a lower initial dose is appropriate, patients may begin treatment with 5 mg once daily in the morning. The maximum recommended dose for children 6-12 years of age is 30 mg/day; doses greater than 30 mg/day of dextroamphetamine saccharate, amphetamine aspartate monohydrate, dextroamphetamine sulfate and amphetamine sulfate extended-release capsules have not been studied in children. Dextroamphetamine saccharate, amphetamine aspartate monohydrate, dextroamphetamine sulfate and amphetamine sulfate extended-release capsules has not been studied in children under 6 years of age.

2.4 Adolescents

The recommended starting dose for adolescents with ADHD who are 13-17 years of age and are either starting treatment for the first time or switching from another medication is 10 mg/day. The dose may be increased to 20 mg/day after one week if ADHD symptoms are not adequately controlled.

2.5 Adults

In adults with ADHD who are either starting treatment for the first time or switching from another medication, the recommended dose is 20 mg/day.

2.6 Dosage in Patients with Renal Impairment

In adult patients with severe renal impairment (GFR 15 to < 30 mL/min/1.73m^2), the recommended dose is 15 mg once daily in the morning. In pediatric patients (6 to 17 years of age) with severe renal impairment, the recommended dose is 5 mg once daily. The maximum dose for children 6 to 12 years of age with severe renal impairment is 20 mg once daily. Dextroamphetamine saccharate, amphetamine aspartate monohydrate, dextroamphetamine sulfate and amphetamine sulfate extended-release capsules is not recommended in patients with end stage renal disease (ESRD) (GFR < 15 mL/min/1.73m^2) [see Use in Specific Populations (8.6), Clinical Pharmacology (12.3)].

3 DOSAGE FORMS AND STRENGTHS

Dextroamphetamine saccharate, amphetamine aspartate monohydrate, dextroamphetamine sulfate and amphetamine sulfate extended-release capsules 5 mg: Capsule with white opaque body and lime green cap (imprinted 5 mg on body and ELI-510 on cap with black ink). Capsules filled with orange pellets.

Dextroamphetamine saccharate, amphetamine aspartate monohydrate, dextroamphetamine sulfate and amphetamine sulfate extended-release capsules 10 mg: Capsule with blue body and blue cap (imprinted 10 mg on body and ELI-511 on cap with black ink). Capsule filled with orange pellets.

Dextroamphetamine saccharate, amphetamine aspartate monohydrate, dextroamphetamine sulfate and amphetamine sulfate extended-release capsules 15 mg: Capsule with white opaque body and green cap (imprinted 15 mg on body and ELI-512 on cap with black ink). Capsule filled with orange pellets.

Dextroamphetamine saccharate, amphetamine aspartate monohydrate, dextroamphetamine sulfate and amphetamine sulfate extended-release capsules 20 mg: Capsule with white opaque body and light pink cap (imprinted 20 mg on body and ELI-513 on cap with black ink). Capsule filled with orange pellets.

Dextroamphetamine saccharate, amphetamine aspartate monohydrate, dextroamphetamine sulfate and amphetamine sulfate extended-release capsules 25 mg: Capsule with pink body and pink cap (imprinted 25 mg on body and ELI-514 on cap with black ink). Capsule filled with orange pellets.

Dextroamphetamine saccharate, amphetamine aspartate monohydrate, dextroamphetamine sulfate and amphetamine sulfate extended-release capsules 30 mg: Capsule with white opaque body and dark pink cap (imprinted 30 mg on body and ELI-515 on cap with black ink). Capsule filled with orange pellets.

4 CONTRAINDICATIONS

Dextroamphetamine saccharate, amphetamine aspartate monohydrate, dextroamphetamine sulfate and amphetamine sulfate extended-release capsules administration is contraindicated in patients with the following conditions:

- Advanced arteriosclerosis
- Symptomatic cardiovascular disease
- Moderate to severe hypertension
- Hyperthyroidism
- In patients known to be hypersensitive to amphetamine, or other components of dextroamphetamine saccharate, amphetamine aspartate monohydrate, dextroamphetamine sulfate and amphetamine sulfate extended-release capsules. Hypersensitivity reactions such as angioedema and anaphylactic reactions have been reported in patients treated with other amphetamine products [see Adverse Reactions (6.2)]
- Glaucoma
- Agitated states
- History of drug abuse
- Patients taking monoamine oxidase inhibitors (MAOIs), or within 14 days of stopping MAOIs (including MAOIs such as linezolid or intravenous methylene blue), because of an increased risk of hypertensive crisis [see Warnings and Precautions (5.6) and Drug Interactions (7.1)]

5 WARNINGS AND PRECAUTIONS

5.1 Potential for Abuse and Dependence

CNS stimulants, including dextroamphetamine saccharate, amphetamine aspartate monohydrate, dextroamphetamine sulfate and amphetamine sulfate extended-release capsules, other amphetamine-containing products, and methylphenidate, have a high potential for abuse and dependence. Assess the risk of abuse prior to prescribing, and monitor for signs of abuse and dependence while on therapy [see Boxed Warning, Drug Abuse and Dependence (9.2, 9.3)].

5.2 Serious Cardiovascular Reactions

Sudden Death and Pre-existing Structural Cardiac Abnormalities or Other Serious Heart Problems

Childrenand Adolescents

Sudden death has been reported in association with CNS stimulant treatment at usual doses in children and adolescents with structural cardiac abnormalities or other serious heart problems. Although some serious heart problems alone carry an increased risk of sudden death, stimulant products generally should not be used in children or adolescents with known serious structural cardiac abnormalities, cardiomyopathy, serious heart rhythm abnormalities, or other serious cardiac problems that may place them at increased vulnerability to the sympathomimetic effects of a stimulant drug [see Contraindications (4)].

Adults

Sudden deaths, stroke, and myocardial infarction have been reported in adults taking stimulant drugs at usual doses for ADHD. Although the role of stimulants in these adult cases is also unknown, adults have a greater likelihood than children of having serious structural cardiac abnormalities, cardiomyopathy, serious heart rhythm abnormalities, coronary artery disease, or other serious cardiac problems. Adults with such abnormalities should also generally not be treated with stimulant drugs [see Contraindications (4)].

Hypertension and Other Cardiovascular Conditions

Stimulant medications cause a modest increase in average blood pressure (about 2-4 mmHg) and average heart rate (about 3-6 bpm), and individuals may have larger increases. While the mean changes alone would not be expected to have short-term consequences, all patients should be monitored for larger changes in heart rate and blood pressure. Caution is indicated in treating patients whose underlying medical conditions might be compromised by increases in blood pressure or heart rate, e.g., those with pre-existing hypertension, heart failure, recent myocardial infarction, or ventricular arrhythmia [see Contraindications (4) and Adverse Reactions (6)].

Assessing Cardiovascular Status in Patients being Treated with Stimulant Medications

Children, adolescents, or adults who are being considered for treatment with stimulant medications should have a careful history (including assessment for a family history of sudden death or ventricular arrhythmia) and physical exam to assess for the presence of cardiac disease, and should receive further cardiac evaluation if findings suggest such disease (e.g. electrocardiogram and echocardiogram). Patients who develop symptoms such as exertional chest pain, unexplained syncope, or other symptoms suggestive of cardiac disease during stimulant treatment should undergo a prompt cardiac evaluation.

5.3 Psychiatric Adverse Events

Pre-Existing Psychosis

Administration of stimulants may exacerbate symptoms of behavior disturbance and thought disorder in patients with pre-existing psychotic disorder.

Bipolar Illness

Particular care should be taken in using stimulants to treat ADHD patients with comorbid bipolar disorder because of concern for possible induction of mixed/manic episode in such patients. Prior to initiating treatment with a stimulant, patients with comorbid depressive symptoms should be adequately screened to determine if they are at risk for bipolar disorder; such screening should include a detailed psychiatric history, including a family history of suicide, bipolar disorder, and depression.

Emergence of New Psychotic or Manic Symptoms

Treatment-emergent psychotic or manic symptoms, e.g., hallucinations, delusional thinking, or mania in children and adolescents without prior history of psychotic illness or mania can be caused by stimulants at usual doses. If such symptoms occur, consideration should be given to a possible causal role of the stimulant, and discontinuation of treatment may be appropriate. In a pooled analysis of multiple short- term, placebo-controlled studies, such symptoms occurred in about 0.1% (4 patients with events out of 3482 exposed to methylphenidate or amphetamine for several weeks at usual doses) of stimulant-treated patients compared to 0 in placebo-treated patients.

Aggression

Aggressive behavior or hostility is often observed in children and adolescents with ADHD, and has been reported in clinical trials and the postmarketing experience of some medications indicated for the treatment of ADHD. Although there is no systematic evidence that stimulants cause aggressive behavior or hostility, patients beginning treatment for ADHD should be monitored for the appearance of or worsening of aggressive behavior or hostility.

5.4 Long-Term Suppression of Growth

Monitor growth in children during treatment with stimulants. Patients who are not growing or gaining weight as expected may need to have their treatment interrupted.

Careful follow-up of weight and height in children ages 7 to 10 years who were randomized to either methylphenidate or non-medication treatment groups over 14 months, as well as in naturalistic subgroups of newly methylphenidate-treated and non-medication treated children over 36 months (to the ages of 10 to 13 years), suggests that consistently medicated children (i.e., treatment for 7 days per week throughout the year) have a temporary slowing in growth rate (on average, a total of about 2 cm less growth in height and 2.7 kg less growth in weight over 3 years), without evidence of growth rebound during this period of development.

In a controlled trial of dextroamphetamine saccharate, amphetamine aspartate monohydrate, dextroamphetamine sulfate and amphetamine sulfate extended-release capsules in adolescents, mean weight change from baseline within the initial 4 weeks of therapy was -1.1 lbs. and -2.8 lbs., respectively, for patients receiving 10 mg and 20 mg dextroamphetamine saccharate, amphetamine aspartate monohydrate, dextroamphetamine sulfate and amphetamine sulfate extended-release capsules. Higher doses were associated with greater weight loss within the initial 4 weeks of treatment. Chronic use of amphetamines can be expected to cause a similar suppression of growth.

5.5 Seizures

There is some clinical evidence that stimulants may lower the convulsive threshold in patients with prior history of seizures, in patients with prior EEG abnormalities in the absence of seizures, and very rarely, in patients without a history of seizures and no prior EEG evidence of seizures. In the presence of seizures, dextroamphetamine saccharate, amphetamine aspartate monohydrate, dextroamphetamine sulfate and amphetamine sulfate extended-release capsules should be discontinued.

5.6 Peripheral Vasculopathy, including Raynaud's phenomenon

Stimulants, including dextroamphetamine saccharate, amphetamine aspartate monohydrate, dextroamphetamine sulfate and amphetamine sulfate extended-release capsules, used to treat ADHD are associated with peripheral vasculopathy, including Raynaud's phenomenon. Signs and symptoms are usually intermittent and mild; however, very rare sequelae include digital ulceration and/or soft tissue breakdown. Effects of peripheral vasculopathy, including Raynaud's phenomenon, were observed in post-marketing reports at different times and at therapeutic doses in all age groups throughout the course of treatment. Signs and symptoms generally improve after reduction in dose or discontinuation of drug. Careful observation for digital changes is necessary during treatment with ADHD stimulants. Further clinical evaluation (e.g., rheumatology referral) may be appropriate for certain patients.

5.7 Serotonin Syndrome

Serotonin syndrome, a potentially life-threatening reaction, may occur when amphetamines are used in combination with other drugs that affect the serotonergic neurotransmitter systems such as MAOIs, selective serotonin reuptake inhibitors (SSRIs), serotonin norepinephrine reuptake inhibitors (SNRIs), triptans, tricyclic antidepressants, fentanyl, lithium, tramadol, tryptophan, buspirone, and St. John's Wort [see Drug Interactions (7.1)]. Amphetamines and amphetamine derivatives are known to be metabolized, to some degree, by cytochrome P450 2D6 (CYP2D6) and display minor inhibition of CYP2D6 metabolism [see Clinical Pharmacology (12.3)]. The potential for a pharmacokinetic interaction exists with the co-administration of CYP2D6 inhibitors which may increase the risk with increased exposure to dextroamphetamine saccharate, amphetamine aspartate monohydrate, dextroamphetamine sulfate and amphetamine sulfate extended-release capsules. In these situations, consider an alternative non-serotonergic drug or an alternative drug that does not inhibit CYP2D6 [see Drug Interactions (7.1)]. Serotonin syndrome symptoms may include mental status changes (e.g., agitation, hallucinations, delirium, and coma), autonomic instability (e.g., tachycardia, labile blood pressure, dizziness, diaphoresis, flushing, hyperthermia), neuromuscular symptoms (e.g., tremor, rigidity, myoclonus, hyperreflexia, incoordination), seizures, and/or gastrointestinal symptoms (e.g., nausea, vomiting, diarrhea).

Concomitant use of dextroamphetamine saccharate, amphetamine aspartate monohydrate, dextroamphetamine sulfate and amphetamine sulfate extended-release capsules with MAOI drugs is contraindicated [see Contraindications (4)].

Discontinue treatment with dextroamphetamine saccharate, amphetamine aspartate monohydrate, dextroamphetamine sulfate and amphetamine sulfate extended-release capsules and any concomitant serotonergic agents immediately if symptoms of serotonin syndrome occur, and initiate supportive symptomatic treatment. Concomitant use of dextroamphetamine saccharate, amphetamine aspartate monohydrate, dextroamphetamine sulfate and amphetamine sulfate extended-release capsules with other serotonergic drugs or CYP2D6 inhibitors should be used only if the potential benefit justifies the potential risk. If clinically warranted, consider initiating dextroamphetamine saccharate, amphetamine aspartate monohydrate, dextroamphetamine sulfate and amphetamine sulfate extended-release capsules with lower doses, monitoring patients for the emergence of serotonin syndrome during drug initiation or titration, and informing patients of the increased risk for serotonin syndrome.

5.8 Visual Disturbance

Difficulties with accommodation and blurring of vision have been reported with stimulant treatment.

5.9 Tics

Amphetamines have been reported to exacerbate motor and phonic tics and Tourette's syndrome. Therefore, clinical evaluation for tics and Tourette's syndrome in patients and their families should precede use of stimulant medications.

5.10 Prescribing and Dispensing

The least amount of amphetamine feasible should be prescribed or dispensed at one time in order to minimize the possibility of overdosage. Dextroamphetamine saccharate, amphetamine aspartate monohydrate, dextroamphetamine sulfate and amphetamine sulfate extended-release capsules should be used with caution in patients who use other sympathomimetic drugs.

6 ADVERSE REACTIONS

Because clinical trials are conducted under widely varying conditions, adverse reaction rates observed in the clinical trials of a drug cannot be directly compared to rates in the clinical trials of another drug and may not reflect the rates observed in clinical practice.

6.1 Clinical Trials Experience

The premarketing development program for dextroamphetamine saccharate, amphetamine aspartate monohydrate, dextroamphetamine sulfate and amphetamine sulfate extended-release capsules included exposures in a total of 1315 participants in clinical trials (635 pediatric patients, 350 adolescent patients, 248 adult patients, and 82 healthy adult subjects). Of these, 635 patients (ages 6 to 12) were evaluated in two controlled clinical studies, one open-label clinical study, and two single-dose clinical pharmacology studies (N= 40). Safety data on all patients are included in the discussion that follows. Adverse reactions were assessed by collecting adverse reactions, results of physical examinations, vital signs, weights, laboratory analyses, and ECGs.
Adverse reactions during exposure were obtained primarily by general inquiry and recorded by clinical investigators using terminology of their own choosing. Consequently, it is not possible to provide a meaningful estimate of the proportion of individuals experiencing adverse reactions without first grouping similar types of reactions into a smaller number of standardized event categories. In the tables and listings that follow, COSTART terminology has been used to classify reported adverse reactions.
The stated frequencies of adverse reactions represent the proportion of individuals who experienced, at least once, a treatment-emergent adverse event of the type listed.
Adverse Reactions Leading to Discontinuation of Treatment
In two placebo-controlled studies of up to 5 weeks duration among children with ADHD, 2.4% (10/425) of dextroamphetamine saccharate, amphetamine aspartate monohydrate, dextroamphetamine sulfate and amphetamine sulfate extended-release capsule-treated patients discontinued due to adverse reactions (including 3 patients with loss of appetite, one of whom also reported insomnia) compared to 2.7% (7/259) receiving placebo.
The most frequent adverse reactions leading to discontinuation of dextroamphetamine saccharate, amphetamine aspartate monohydrate, dextroamphetamine sulfate and amphetamine sulfate extended-release capsules in controlled and uncontrolled, multiple-dose clinical trials of children (N=595) were anorexia (loss of appetite) (2.9%), insomnia (1.5%), weight loss (1.2%), emotional lability (1%), and depression (0.7%). Over half of these patients were exposed to dextroamphetamine saccharate, amphetamine aspartate monohydrate, dextroamphetamine sulfate and amphetamine sulfate extended-release capsules for 12 months or more.
In a separate placebo-controlled 4-week study in adolescents with ADHD, five patients (2.1%) discontinued treatment due to adverse events among dextroamphetamine saccharate, amphetamine aspartate monohydrate, dextroamphetamine sulfate and amphetamine sulfate extended-release capsule-treated patients (N=233) compared to none who received placebo (N=54). The most frequent adverse event leading to discontinuation and considered to be drug-related (i.e. leading to discontinuation in at least 1% of dextroamphetamine saccharate, amphetamine aspartate monohydrate, dextroamphetamine sulfate and amphetamine sulfate extended-release capsule-treated patients and at a rate at least twice that of placebo) was insomnia (1.3%, n=3).
In one placebo-controlled 4-week study among adults with ADHD with doses 20 mg to 60 mg, 23 patients (12.0%) discontinued treatment due to adverse events among dextroamphetamine saccharate, amphetamine aspartate monohydrate, dextroamphetamine sulfate and amphetamine sulfate extended-release capsule-treated patients (N=191) compared to one patient (1.6%) who received placebo (N=64). The most frequent adverse events leading to discontinuation and considered to be drug-related (i.e. leading to discontinuation in at least 1% of dextroamphetamine saccharate, amphetamine aspartate monohydrate, dextroamphetamine sulfate and amphetamine sulfate extended-release capsule-treated patients and at a rate at least twice that of placebo) were insomnia (5.2%, n=10), anxiety (2.1%, n=4), nervousness (1.6%, n=3), dry mouth (1.6%, n=3), anorexia (1.6%, n=3), tachycardia (1.6%, n=3), headache (1.6%, n=3), and asthenia (1.0%, n=2).
Adverse Reactions Occurring in Controlled Trials
Adverse reactions reported in a 3-week clinical trial of children and a 4-week clinical trial in adolescents and adults, respectively, treated with dextroamphetamine saccharate, amphetamine aspartate monohydrate, dextroamphetamine sulfate and amphetamine sulfate extended-release capsules or placebo are presented in the tablets below.

Table 1 Adverse Reactions Reported by 2% or More of Children (6-12 Years Old) Receiving dextroamphetamine saccharate, amphetamine aspartate monohydrate, dextroamphetamine sulfate and amphetamine sulfate extended-release capsules with Higher Incidence Than on Placebo in a 584-Patient Clinical Study

Body System | Preferred Term | Dextroamphetamine saccharate, amphetamine aspartate monohydrate, dextroamphetamine sulfate and amphetamine sulfate extended-release capsules (n=374) | Placebo (n=210)
General | Abdominal Pain (stomachache); Fever; Infection; Accidental Injury; Asthenia (fatigue) | 14%; 5%; 4%; 3%; 2% | 10%; 2%; 2%; 2%; 0%
Digestive System | Loss of Appetite; Vomiting; Nausea; Dyspepsia | 22%; 7%; 5%; 2% | 2%; 4%; 3%; 1%
Nervous System | Insomnia; Emotional Lability; Nervousness; Dizziness | 17%; 9%; 6%; 2% | 2%; 2%; 2%; 0%
Metabolic/ Nutritional | Weigh Loss | 4% | 0%

Table 2 Adverse Reactions Reported by 5% or More of Adolescents (13-17 Years Old) Weighing ≤ 75 kg/165 lbs Receiving dextroamphetamine saccharate, amphetamine aspartate monohydrate, dextroamphetamine sulfate and amphetamine sulfate extended-release capsules with Higher Incidence Than Placebo in a 287 Patient Clinical Forced Weekly-Dose Titration Study*

Body System | Preferred Term | Dextroamphetamine saccharate, amphetamine aspartate monohydrate, dextroamphetamine sulfate and amphetamine sulfate extended-release capsules (n=233) | Placebo (n=54)
General | Abdominal Pain (stomachache) | 11% | 2%
Digestive System | Loss of Appetiteb | 36% | 2%
Nervous System | Insomniab Nervousness | 12% 6% | 4% 6%a
Metabolic/Nutritional | Weight Lossb | 9% | 0%

*Included doses up to 40 mg

a Appears the same due to rounding

b Dose-related adverse reactions

Note: The following reactions did not meet the criterion for inclusion in Table 2 but were reported by 2% to 4% of adolescent patients receiving dextroamphetamine saccharate, amphetamine aspartate monohydrate, dextroamphetamine sulfate and amphetamine sulfate extended-release capsules with a higher incidence than patients receiving placebo in this study: accidental injury, asthenia (fatigue), dry mouth, dyspepsia, emotional lability, nausea, somnolence, and vomiting.

Table 3 Adverse Reactions Reported by 5% or More of Adults Receiving Dextroamphetamine saccharate, amphetamine aspartate monohydrate, dextroamphetamine sulfate and amphetamine sulfate extended-release capsules with Higher Incidence Than on Placebo in a 255 Patient Clinical Forced Weekly-Dose Titration Study*

Body System | Preferred Term | Dextroamphetamine saccharate, amphetamine aspartate monohydrate, dextroamphetamine sulfate and amphetamine sulfate extended-release capsules (n=191) | Placebo (n=64)
General | Headache; Asthensia | 26%; 6% | 13%; 5%
Digestive System | Dry Mouth; Loss of Appetite; Nausea; Diarrhea | 35%; 33%; 8%; 6% | 5%; 3%; 3%; 0%
Nervous System | Insomnia; Agitation; Anxiety; Dizziness; Nervousness | 27%; 8%; 8%; 7%; 13% | 13%; 5%; 5%; 0%; 13%a
Cardiovascular System | Tachycardia | 6% | 3%
Metabolic/Nutritional | Weight Loss | 10% | 0%
Urogenital System | Urinary Tract Infection | 5% | 0%

*Included doses up to 60 mg.

aAppears the same due to rounding

Note: The following reactions did not meet the criterion for inclusion in Table 3 but were reported by 2% to 4% of adult patients receiving dextroamphetamine saccharate, amphetamine aspartate monohydrate, dextroamphetamine sulfate and amphetamine sulfate extended-release capsules with a higher incidence than patients receiving placebo in this study: infection, photosensitivity reaction, constipation, tooth disorder (e.g., teeth clenching, tooth infection), emotional lability, libido decreased, somnolence, speech disorder (e.g., stuttering, excessive speech), palpitation, twitching, dyspnea, sweating, dysmenorrhea, and impotence.

Hypertension [ see Warnings and Precautions (5.3)]

In a controlled 4-week outpatient clinical study of adolescents with ADHD, isolated systolic blood pressure elevations ≥15 mmHg were observed in 7/64 (11%) placebo-treated patients and 7/100 (7%) patients receiving dextroamphetamine saccharate, amphetamine aspartate monohydrate, dextroamphetamine sulfate and amphetamine sulfate extended-release capsules 10 or 20 mg. Isolated elevations in diastolic blood pressure ≥ 8 mmHg were observed in 16/64 (25%) placebo-treated patients and 22/100 (22%) dextroamphetamine saccharate, amphetamine aspartate monohydrate, dextroamphetamine sulfate and amphetamine sulfate extended-release capsule-treated patients. Similar results were observed at higher doses.

In a single-dose pharmacokinetic study in 23 adolescents with ADHD, isolated increases in systolic blood pressure (above the upper 95% CI for age, gender, and stature) were observed in 2/17 (12%) and 8/23 (35%), subjects administered 10 mg and 20 mg dextroamphetamine saccharate, amphetamine aspartate monohydrate, dextroamphetamine sulfate and amphetamine sulfate extended-release capsules, respectively. Higher single doses were associated with a greater increase in systolic blood pressure. All increases were transient, appeared maximal at 2 to 4 hours post dose and not associated with symptoms.

6.2 Adverse Reactions Associated with the Use of Amphetamine, dextroamphetamine saccharate, amphetamine aspartate monohydrate, dextroamphetamine sulfate and amphetamine sulfate extended-release capsules, or dextroamphetamine saccharate, amphetamine aspartate monohydrate, dextroamphetamine sulfate and amphetamine sulfate tablets

The following adverse reactions have been identified during post-approval use of amphetamine, dextroamphetamine saccharate, amphetamine aspartate monohydrate, dextroamphetamine sulfate and amphetamine sulfate extended-release capsules, or dextroamphetamine saccharate, amphetamine aspartate monohydrate, dextroamphetamine sulfate and amphetamine sulfate tablets. Because these reactions are reported voluntarily from a population of uncertain size, it is not always possible to reliably estimate their frequency or establish a causal relationship to drug exposure.

Cardiovascular
Palpitations. There have been isolated reports of cardiomyopathy associated with chronic amphetamine use.
Central Nervous System
Psychotic episodes at recommended doses, overstimulation, restlessness, irritability, euphoria, dyskinesia, dysphoria, depression, tremor, tics, aggression, anger, logorrhea, dermatillomania, paresthesia (including formication), and bruxism.
Eye Disorders
Vision blurred, mydriasis.
Gastrointestinal
Unpleasant taste, constipation, other gastrointestinal disturbances.
Allergic
Urticaria, rash, hypersensitivity reactions including angioedema and anaphylaxis. Serious skin rashes, including Stevens-Johnson Syndrome and toxic epidermal necrolysis have been reported.
Endocrine
Impotence, changes in libido, frequent or prolonged erections.
Skin
Alopecia.
Vascular Disorders
Raynaud's phenomenon.
Musculoskeletal and Connective Tissue Disorders
Rhabdomyolysis

7 DRUG INTERACTIONS

7.1 Clinically Important Interactions with Amphetamines

Table 4: Drugs Having Clinically Important Interactions with Amphetamines
Monoamine Oxidase Inhibitors (MAOIs)
Clinical Impact | Concomitant use of MAOIs and CNS stimulants can cause hypertensive crisis. Potential outcomes include death, stroke, myocardial infarction, aortic dissection, ophthalmological complications, eclampsia, pulmonary edema, and renal failure.
Intervention | Do not administer dextroamphetamine saccharate, amphetamine aspartate monohydrate, dextroamphetamine sulfate and amphetamine sulfate extended-release capsules concomitantly or within 14 days after discontinuing MAOI [see Contraindications (4)]
Serotonergic Drugs
Clinical Impact | The concomitant use of dextroamphetamine saccharate, amphetamine aspartate monohydrate, dextroamphetamine sulfate and amphetamine sulfate extended-release capsules and serotonergic drugs increases the risk of serotonin syndrome.
Intervention | Initiate with lower doses and monitor patients for signs and symptoms of serotonin syndrome, particularly during dextroamphetamine saccharate, amphetamine aspartate monohydrate, dextroamphetamine sulfate and amphetamine sulfate extended-release capsules initiation or dosage increase. If serotonin syndrome occurs, discontinue dextroamphetamine saccharate, amphetamine aspartate monohydrate, dextroamphetamine sulfate and amphetamine sulfate extended-release capsules and the concomitant serotonergic drug(s) [see Warnings and Precautions (5.6) ].
Examples | selective serotonin reuptake inhibitors (SSRI), serotonin norepinephrine reuptake inhibitors (SNRI), triptans, tricyclic antidepressants, fentanyl, lithium, tramadol, tryptophan, buspirone, St. John's Wort
xxxCYPD26 Inhibitors
Clinical Impact | The concomitant use of dextroamphetamine saccharate, amphetamine aspartate monohydrate, dextroamphetamine sulfate and amphetamine sulfate extended-release capsules and CYP2D6 inhibitors may increase the exposure of dextroamphetamine saccharate, amphetamine aspartate monohydrate, dextroamphetamine sulfate and amphetamine sulfate extended-release capsules compared to the use of the drug alone and increase the risk of serotonin syndrome.
Intervention | Initiate with lower doses and monitor patients for signs and symptoms of serotonin syndrome particularly during dextroamphetamine saccharate, amphetamine aspartate monohydrate, dextroamphetamine sulfate and amphetamine sulfate extended-release capsules initiation and after a dosage increase. If serotonin syndrome occurs, discontinue dextroamphetamine saccharate, amphetamine aspartate monohydrate, dextroamphetamine sulfate and amphetamine sulfate extended-release capsules and the CYP2D6 inhibitor [see Warnings and Precautions (5.6) and Overdosage (10) ].
Examples | paroxetine and fluoxetine (also serotonergic drugs), quinidine, ritonavir
Alkalinizing Agents
Clinical Impact | Increase blood levels and potentiate the action of amphetamine.
Intervention | Co-administration of dextroamphetamine saccharate, amphetamine aspartate monohydrate, dextroamphetamine sulfate and amphetamine sulfate extended-release capsules and gastrointestinal or urinary alkalinizing agents should be avoided.
Examples | Gastrointestinal alkalinizing agents (e.g., sodium bicarbonate). Urinary alkalinizing agents (e.g. acetazolamide, some thiazides).
Acidifying Agents
Clinical Impact | Lower blood levels and efficacy of amphetamines.
Intervention | Increase dose based on clinical response.
Examples | Gastrointestinal acidifying agents (e.g., guanethidine, reserpine, glutamic acid HCl, ascorbic acid). Urinary acidifying agents (e.g., ammonium chloride, sodium acid phosphate, methenamine salts).
Tricyclic Antidepressants
Clinical Impact | May enhance the activity of tricyclic or sympathomimetic agents causing striking and sustained increases in the concentration of d-amphetamine in the brain; cardiovascular effects can be potentiated.
Intervention | Monitor frequently and adjust or use alternative therapy based on clinical response.
Examples | desipramine, protriptyline
Proton Pump Inhibors
Clinical Impact | Time to maximum concentration (Tmax) of amphetamine is decreased compared to when administered alone.
Intervention | Monitor patients for changes in clinical effect and adjust therapy based on clinical response.
Examples | Omeprazole

8 USE IN SPECIFIC POPULATIONS

8.1 Pregnancy

Pregnancy Exposure Registry

There is a pregnancy exposure registry that monitors pregnancy outcomes in women exposed to dextroamphetamine saccharate, amphetamine aspartate monohydrate, dextroamphetamine sulfate and amphetamine sulfate extended-release capsules during pregnancy. Healthcare providers are encouraged to register patients by calling the National Pregnancy Registry for Psychostimulants at 1-866-961-2388 or visiting online at https://womensmentalhealth.org/clinical-and-research-programs/pregnancyregistry/othermedications/.

Risk Summary

Available data from published epidemiologic studies and postmarketing reports on use of prescription amphetamine in pregnant women have not identified a drug-associated risk of major birth defects and miscarriage (see Data). Adverse pregnancy outcomes, including premature delivery and low birth weight, have been seen in infants born to mothers taking amphetamines during pregnancy (see Clinical Considerations).

No apparent effects on morphological development were observed in embryo-fetal development studies, with oral administration of amphetamine to rats and rabbits during organogenesis at doses 2 and 12 times, respectively, the maximum recommended human dose (MRHD) of 20 mg/day given to adolescents, on a mg/m^2 basis. However, in a pre- and post-natal development study, amphetamine (d- to l- ratio of 3:1) administered orally to pregnant rats during gestation and lactation caused a decrease in pup survival and a decrease in pup body weight that correlated with a delay in developmental landmarks at clinically relevant doses of amphetamine. In addition, adverse effects on reproductive performance were observed in pups whose mothers were treated with amphetamine. Long-term neurochemical and behavioral effects have also been reported in animal developmental studies using clinically relevant doses of amphetamine (see Data).

The estimated background risk of major birth defects and miscarriage for the indicated population is unknown. All pregnancies have a background risk of birth defect, loss, or other adverse outcomes. In the U.S. general population, the estimated background risk of major birth defects and miscarriage in clinically recognized pregnancies is 2-4% and 15- 20%, respectively.

Clinical Considerations

Fetal/Neonatal Adverse Reactions

Amphetamines, such as dextroamphetamine saccharate, amphetamine aspartate monohydrate, dextroamphetamine sulfate and amphetamine sulfate extended-release capsules, cause vasoconstriction and thereby may decrease placental perfusion. In addition, amphetamines can stimulate uterine contractions, increasing the risk of premature delivery. Infants born to mothers taking amphetamines during pregnancy have an increased risk of premature delivery and low birth weight.

Monitor infants born to mothers taking amphetamines for symptoms of withdrawal such as feeding difficulties, irritability, agitation, and excessive drowsiness.

Data

Animal Data

Amphetamine (d- to l- enantiomer ratio of 3:1), had no apparent effects on embryofetal morphological development or survival when administered orally to pregnant rats and rabbits throughout the period of organogenesis at doses of up to 6 and 16 mg/kg/day, respectively. These doses are approximately 2 and 12 times, respectively, the maximum recommended human dose (MRHD) of 20 mg/day given to adolescents, on a mg/m^2 basis. Fetal malformations and death have been reported in mice following parenteral administration of d-amphetamine doses of 50 mg/kg/day (approximately 10 times the MRHD given to adolescents on a mg/m^2 basis) or greater to pregnant animals. Administration of these doses was also associated with severe maternal toxicity.

A study was conducted in which pregnant rats received daily oral doses of amphetamine (d- to l- enantiomer ratio of 3:1) of 2, 6, and 10 mg/kg from gestation day 6 to lactation day 20. These doses are approximately 0.8, 2, and 4 times the MRHD of 20 mg/day given to adolescents, on a mg/m^2 basis. All doses caused hyperactivity and decreased weight gain in the dams. A decrease in pup survival was seen at all doses. A decrease in pup body weight was seen at 6 and 10 mg/kg which correlated with delays in developmental landmarks, such as preputial separation and vaginal opening. Increased pup locomotor activity was seen at 10 mg/kg on day 22 postpartum but not at 5 weeks postweaning. When pups were tested for reproductive performance at maturation, gestational weight gain, number of implantations, and number of delivered pups were decreased in the group whose mothers had been given 10 mg/kg.

A number of studies from the literature in rodents indicate that prenatal or early postnatal exposure to amphetamine (d- or d, l-), at doses similar to those used clinically can result in long-term neurochemical and behavioral alterations. Reported behavioral effects include learning and memory deficits, altered locomotor activity, and changes in sexual function.

8.2 Lactation

Risk Summary

Based on limited case reports in published literature, amphetamine (d- or d, l-) is present in human milk, at relative infant doses of 2% to 13.8% of the maternal weight-adjusted dosage and a milk/plasma ratio ranging between 1.9 and 7.5. There are no reports of adverse effects on the breastfed infant. Long-term neurodevelopmental effects on infants from amphetamine exposure are unknown. It is possible that large dosages of amphetamine might interfere with milk production, especially in women whose lactation is not well established. Because of the potential for serious adverse reactions in nursing infants, advise patients that breastfeeding is not recommended during treatment with dextroamphetamine saccharate, amphetamine aspartate monohydrate, dextroamphetamine sulfate and amphetamine sulfate extended-release capsules.

8.4 Pediatric Use

Dextroamphetamine saccharate, amphetamine aspartate monohydrate, dextroamphetamine sulfate and amphetamine sulfate extended-release capsules is indicated for use in children 6 years of age and older.

The safety and efficacy of dextroamphetamine saccharate, amphetamine aspartate monohydrate, dextroamphetamine sulfate and amphetamine sulfate extended-release capsules in children under 6 years of age have not been studied. Long-term effects of amphetamines in children have not been well established.

Long-Term Growth Suppression

Growth should be monitored during treatment with stimulants, including dextroamphetamine saccharate, amphetamine aspartate monohydrate, dextroamphetamine sulfate and amphetamine sulfate extended-release capsules, and pediatric patients aged 6 to 17 years who are not growing or gaining weight as expected may need to have their treatment interrupted [see Warnings and Precautions (5.3)].

Juvenile Animal Toxicity Data

Juvenile rats treated with mixed amphetamine salts early in the postnatal period through sexual maturation demonstrated transient changes in motor activity. Learning and memory was impaired at approximately 6 times the maximum recommended human dose (MRHD) given to children on a mg/m^2 basis. No recovery was seen following a drug free period. A delay in sexual maturation was observed at a dose approximately 6 times the MRHD given to children on a mg/m^2 basis, although there was no effect on fertility.

In a juvenile developmental study, rats received daily oral doses of amphetamine (d to l enantiomer ratio of 3:1) of 2, 6, or 20 mg/kg on days 7-13 of age; from day 14 to approximately day 60 of age these doses were given b.i.d. for total daily doses of 4, 12, or 40 mg/kg. The latter doses are approximately 0.6, 2, and 6 times the MRHD of 30 mg/day, given to children on a mg/m^2 basis. Post dosing hyperactivity was seen at all doses; motor activity measured prior to the daily dose was decreased during the dosing period but the decreased motor activity was largely absent after an 18 day drug-free recovery period. Performance in the Morris water maze test for learning and memory was impaired at the 40 mg/kg dose, and sporadically at the lower doses, when measured prior to the daily dose during the treatment period; no recovery was seen after a 19 day drug-free period. A delay in the developmental milestones of vaginal opening and preputial separation was seen at 40 mg/kg but there was no effect on fertility.

8.5 Geriatric Use

Dextroamphetamine saccharate, amphetamine aspartate monohydrate, dextroamphetamine sulfate and amphetamine sulfate extended-release capsules has not been studied in the geriatric population.

8.6 Renal Impairment

Due to reduced clearance of amphetamines in patients with severe renal impairment (GFR 15 to < 30 mL/min/1.73m^2), the recommended dose should be reduced. Dextroamphetamine saccharate, amphetamine aspartate monohydrate, dextroamphetamine sulfate and amphetamine sulfate extended-release capsules are not recommended in patients with ESRD (GFR < 15 mL/min/1.73m^2) [see Dosage and Administration (2.5), Clinical Pharmacology (12.3)].

d-Amphetamine is not dialyzable.

9 DRUG ABUSE AND DEPENDENCE

9.1 Controlled Substance

Dextroamphetamine saccharate, amphetamine aspartate monohydrate, dextroamphetamine sulfate and amphetamine sulfate extended-release capsules is a Schedule II controlled substance.

9.2 Abuse

Dextroamphetamine saccharate, amphetamine aspartate monohydrate, dextroamphetamine sulfate and amphetamine sulfate extended-release capsules is a CNS stimulant that contains amphetamine, which has a high potential for abuse. Abuse is characterized by impaired control of drug use, compulsive use despite harm, and craving.

Signs and symptoms of amphetamine abuse may include increased heart rate, respiratory rate, blood pressure, and/or sweating, dilated pupils, hyperactivity, restlessness, insomnia, decreased appetite, loss of coordination, tremors, flushed skin, vomiting, and/or abdominal pain. Anxiety, psychosis, hostility, aggression, suicidal or homicidal ideation have also been observed. Abusers of amphetamines may use other unapproved routes of administration which can result in overdose and death [see Overdosage (10)].

To reduce the abuse of CNS stimulants, including dextroamphetamine saccharate, amphetamine aspartate monohydrate, dextroamphetamine sulfate and amphetamine sulfate extended-release capsules, assess the risk of abuse prior to prescribing. After prescribing, keep careful prescription records, educate patients and their families about abuse and proper storage and disposal of CNS stimulants. Monitor for signs of abuse while on therapy and re-evaluate the need for dextroamphetamine saccharate, amphetamine aspartate monohydrate, dextroamphetamine sulfate and amphetamine sulfate extended-release capsules use.

9.3 Dependence

Tolerance (a state of adaptation in which exposure to a specific dose of a drug results in a reduction of the drug’s desired and/or undesired effects over time, in such a way that a higher dose of the drug is required to produce the same effect that was once obtained at a lower dose) may occur during chronic therapy of CNS stimulants including dextroamphetamine saccharate, amphetamine aspartate monohydrate, dextroamphetamine sulfate and amphetamine sulfate extended-release capsules.

Physical Dependence (which is manifested by a withdrawal syndrome produced by abrupt cessation, rapid dose reduction, or administration of an antagonist) may occur in patients treated with CNS stimulants including dextroamphetamine saccharate, amphetamine aspartate monohydrate, dextroamphetamine sulfate and amphetamine sulfate extended-release capsules. Withdrawal symptoms after abrupt cessation of CNS stimulants include dysphoric mood; fatigue; vivid, unpleasant dreams; insomnia or hypersomnia; increased appetite; and psychomotor retardation or agitation.

10 OVERDOSAGE

Manifestations of amphetamine overdose include restlessness, tremor, hyperreflexia, rapid respiration, confusion, assaultiveness, hallucinations, panic states, hyperpyrexia and rhabdomyolysis. Fatigue and depression usually follow the central nervous system stimulation. Serotonin syndrome has been reported with amphetamine use, including dextroamphetamine saccharate, amphetamine aspartate monohydrate, dextroamphetamine sulfate and amphetamine sulfate extended-release capsules. Cardiovascular effects include arrhythmias, hypertension or hypotension and circulatory collapse. Gastrointestinal symptoms include nausea, vomiting, diarrhea and abdominal cramps. Fatal poisoning is usually preceded by convulsions and coma.
Treatment
Consult with a Certified Poison Control Center for up to date guidance and advice.
The prolonged release of mixed amphetamine salts from dextroamphetamine saccharate, amphetamine aspartate monohydrate, dextroamphetamine sulfate and amphetamine sulfate extended-release capsules should be considered when treating patients with overdose.

d-Amphetamine is not dialyzable.

11 DESCRIPTION

Dextroamphetamine saccharate, amphetamine aspartate monohydrate, dextroamphetamine sulfate and amphetamine sulfate extended-release capsules contain mixed salts of a single-entity amphetamine, a CNS stimulant. Dextroamphetamine saccharate, amphetamine aspartate monohydrate, dextroamphetamine sulfate and amphetamine sulfate extended-release capsules contains equal amounts (by weight) of four salts: dextroamphetamine sulfate, amphetamine sulfate, dextroamphetamine saccharate and amphetamine (D, L)-aspartate monohydrate. This results in a 3.1:1 mixture of dextro- to levo- amphetamine base equivalent.
The 5 mg, 10 mg, 15 mg, 20 mg, 25 mg and 30 mg strength extended release capsules are for oral administration. Dextroamphetamine saccharate, amphetamine aspartate monohydrate, dextroamphetamine sulfate and amphetamine sulfate extended-release capsules contains two types of drug-containing beads (immediate-release and delayed release) which prolong the release of amphetamine compared to the dextroamphetamine saccharate, amphetamine aspartate monohydrate, dextroamphetamine sulfate and amphetamine sulfate (immediate-release) tablet formulation.

Each Capsule contains:; Capsule Strength | 5 mg | 10 mg | 15 mg | 20 mg | 25 mg | 30 mg
Dextroamphetamine Saccharate | 1.25 mg | 2.5 mg | 3.75 mg | 5.0 mg | 6.25 mg | 7.5 mg
Amphetamine (D,L)- Aspartate Monohydrate | 1.25 mg | 2.5 mg | 3.75 mg | 5.0 mg | 6.25 mg | 7.5 mg
Dextroamphetamine Sulfate USP | 1.25 mg | 2.5 mg | 3.75 mg | 5.0 mg | 6.25 mg | 7.5 mg
Amphetamine Sulfate USP | 1.25 mg | 2.5 mg | 3.75 mg | 5.0 mg | 6.25 mg | 7.5 mg
Total amphetamine base equivalence | 3.1 mg | 6.3 mg | 9.4 mg | 12.5 mg | 15.6 mg | 18.8 mg
d-amphetamine base equivalence | 2.4 mg | 4.7 mg | 7.1 mg | 9.5 mg | 11.9 mg | 14.2 mg
l-amphetamine base equivalence | 0.75 mg | 1.5 mg | 2.3 mg | 3.0 mg | 3.8 mg | 4.5 mg

Inactive Ingredients and Colors
The inactive ingredients in dextroamphetamine saccharate, amphetamine aspartate monohydrate, dextroamphetamine sulfate and amphetamine sulfate extended-release capsules include: ferric oxide red, ferric oxide yellow, gelatin capsules, hypromellose 2910/3 cP, 6 cP and 50 cP, methacrylic acid and ethyl acrylate copolymer, titanium dioxide, polyethylene glycol, polysorbate 80, sugar spheres, talc, and triethyl citrate.
The 5 mg gelatin capsules contain gelatin, titanium dioxide, D&C yellow #10, FD&C blue #1 and FD&C yellow #6.
The 10 mg gelatin capsules contain gelatin, FD&C blue #1, and FD&C red #40.
The 15 mg gelatin capsules contain gelatin, titanium dioxide, FD&C blue #1, and FD&C yellow #6.
The 20 mg gelatin capsules contain gelatin, titanium dioxide, and FD&C red #3.
The 25 mg gelatin capsules contain gelatin, FD&C red #40, and FD&C yellow #6.
The 30 mg gelatin capsules contain gelatin, titanium dioxide, D&C red #28, and FD&C red #40.
The ink ingredients are common for all strengths: the capsule imprint black ink contains FD&C blue #1 aluminum lake, FD&C red #40 aluminum lake, FD&C yellow #6 aluminum lake, propylene glycol, and shellac.

12 CLINICAL PHARMACOLOGY

12.1 Mechanism of Action

Amphetamines are non-catecholamine sympathomimetic amines with CNS stimulant activity. The mode of therapeutic action in ADHD is not known.

12.2 Pharmacodynamics

Amphetamines block the reuptake of norepinephrine and dopamine into the presynaptic neuron and increase the release of these monoamines into the extraneuronal space.

12.3 Pharmacokinetics

harmacokinetic studies of dextroamphetamine saccharate, amphetamine aspartate monohydrate, dextroamphetamine sulfate and amphetamine sulfate extended-release capsules have been conducted in healthy adult and pediatric (children aged 6-12 yrs) subjects, and adolescent (13-17 yrs) and children with ADHD. Both dextroamphetamine saccharate, amphetamine aspartate monohydrate, dextroamphetamine sulfate and amphetamine sulfate (immediate-release) tablets and dextroamphetamine saccharate, amphetamine aspartate monohydrate, dextroamphetamine sulfate and amphetamine sulfate extended-release capsules contain d-amphetamine and l-amphetamine salts in the ratio of 3:1. Following administration of dextroamphetamine saccharate, amphetamine aspartate monohydrate, dextroamphetamine sulfate and amphetamine sulfate tablets (immediate-release), the peak plasma concentrations occurred in about 3 hours for both d-amphetamine and l-amphetamine.
The time to reach maximum plasma concentration (Tmax) for dextroamphetamine saccharate, amphetamine aspartate monohydrate, dextroamphetamine sulfate and amphetamine sulfate extended-release capsules is about 7 hours, which is about 4 hours longer compared to dextroamphetamine saccharate, amphetamine aspartate monohydrate, dextroamphetamine sulfate and amphetamine sulfate tablets (immediate-release). This is consistent with the extended-release nature of the product.

Figure 1 Mean d-amphetamine and l-amphetamine Plasma Concentrations Following Administration of dextroamphetamine saccharate, amphetamine aspartate monohydrate, dextroamphetamine sulfate and amphetamine sulfate extended-release capsules 20 mg (8 am) and dextroamphetamine saccharate, amphetamine aspartate monohydrate, dextroamphetamine sulfate and amphetamine sulfate tablets (immediate-release) 10 mg Twice Daily (8 am and 12 noon) in the Fed State.

A single dose of dextroamphetamine saccharate, amphetamine aspartate monohydrate, dextroamphetamine sulfate and amphetamine sulfate extended-release capsules 20 mg capsules provided comparable plasma concentration profiles of both d-amphetamine and l-amphetamine to dextroamphetamine saccharate, amphetamine aspartate monohydrate, dextroamphetamine sulfate and amphetamine sulfate tablets (immediate-release) 10 mg twice daily administered 4 hours apart.
The mean elimination half-life for d-amphetamine is 10 hours in adults; 11 hours in adolescents aged 13-17 years and weighing less than or equal to 75 kg/165 lbs; and 9 hours in children aged 6 to 12 years. For the l-amphetamine, the mean elimination half-life in adults is 13 hours; 13 to 14 hours in adolescents; and 11 hours in children aged 6 to 12 years. On a mg/kg body weight basis, children have a higher clearance than adolescents or adults (see Special Populations below).
Dextroamphetamine saccharate, amphetamine aspartate monohydrate, dextroamphetamine sulfate and amphetamine sulfate extended-release capsules demonstrates linear pharmacokinetics over the dose range of 20 to 60 mg in adults and adolescents weighing greater than 75 kg/165 lbs, over the dose range of 10 to 40 mg in adolescents weighing less than or equal to 75 kg/165 lbs, and 5 to 30 mg in children aged 6 to 12 years. There is no unexpected accumulation at steady state in children.
Food does not affect the extent of absorption of d-amphetamine and l-amphetamine, but prolongs Tmax by 2.5 hours (from 5.2 hrs at fasted state to 7.7 hrs after a high-fat meal) for d-amphetamine and 2.7 hours (from 5.6 hrs at fasted state to 8.3 hrs after a high fat meal) for l-amphetamine after administration of dextroamphetamine saccharate, amphetamine aspartate monohydrate, dextroamphetamine sulfate and amphetamine sulfate extended-release capsules 30 mg. Opening the capsule and sprinkling the contents on applesauce results in comparable absorption to the intact capsule taken in the fasted state. Equal doses of dextroamphetamine saccharate, amphetamine aspartate monohydrate, dextroamphetamine sulfate and amphetamine sulfate extended-release capsules strengths are bioequivalent.
Metabolism and Excretion
Amphetamine is reported to be oxidized at the 4 position of the benzene ring to form 4-hydroxyamphetamine, or on the side chain α or β carbons to form alpha-hydroxy-amphetamine or norephedrine, respectively. Norephedrine and 4-hydroxy-amphetamine are both active and each is subsequently oxidized to form 4-hydroxy-norephedrine. Alpha-hydroxy-amphetamine undergoes deamination to form phenylacetone, which ultimately forms benzoic acid and its glucuronide and the glycine conjugate hippuric acid. Although the enzymes involved in amphetamine metabolism have not been clearly defined, CYP2D6 is known to be involved with formation of 4-hydroxy-amphetamine. Since CYP2D6 is genetically polymorphic, population variations in amphetamine metabolism are a possibility.
Amphetamine is known to inhibit monoamine oxidase, whereas the ability of amphetamine and its metabolites to inhibit various P450 isozymes and other enzymes has not been adequately elucidated. In vitro experiments with human microsomes indicate minor inhibition of CYP2D6 by amphetamine and minor inhibition of CYP1A2, 2D6, and 3A4 by one or more metabolites. However, due to the probability of auto-inhibition and the lack of information on the concentration of these metabolites relative to in vivo concentrations, no predications regarding the potential for amphetamine or its metabolites to inhibit the metabolism of other drugs by CYP isozymes in vivo can be made.
With normal urine pHs, approximately half of an administered dose of amphetamine is recoverable in urine as derivatives of alpha-hydroxy-amphetamine and approximately another 30-40% of the dose is recoverable in urine as amphetamine itself. Since amphetamine has a pKa of 9.9, urinary recovery of amphetamine is highly dependent on pH and urine flow rates. Alkaline urine pHs result in less ionization and reduced renal elimination, and acidic pHs and high flow rates result in increased renal elimination with clearances greater than glomerular filtration rates, indicating the involvement of active secretion. Urinary recovery of amphetamine has been reported to range from 1% to 75%, depending on urinary pH, with the remaining fraction of the dose hepatically metabolized. Consequently, both hepatic and renal dysfunction have the potential to inhibit the elimination of amphetamine and result in prolonged exposures. In addition, drugs that effect urinary pH are known to alter the elimination of amphetamine, and any decrease in amphetamine's metabolism that might occur due to drug interactions or genetic polymorphisms is more likely to be clinically significant when renal elimination is decreased [see Drug Interactions (7)].
Special Populations
Comparison of the pharmacokinetics of d- and l-amphetamine after oral administration of dextroamphetamine saccharate, amphetamine aspartate monohydrate, dextroamphetamine sulfate and amphetamine sulfate extended-release capsules in children (6-12 years) and adolescent (13-17 years) ADHD patients and healthy adult volunteers indicates that body weight is the primary determinant of apparent differences in the pharmacokinetics of d- and l-amphetamine across the age range. Systemic exposure measured by area under the curve to infinity (AUC∞) and maximum plasma concentration (Cmax) decreased with increases in body weight, while oral volume of distribution (VZ/F), oral clearance (CL/F), and elimination half-life (t1/2) increased with increases in body weight.
Pediatric Patients
On a mg/kg weight basis, children eliminated amphetamine faster than adults. The elimination half-life (t1/2) is approximately 1 hour shorter for d-amphetamine and 2 hours shorter for l-amphetamine in children than in adults. However, children had higher systemic exposure to amphetamine (Cmax and AUC) than adults for a given dose of dextroamphetamine saccharate, amphetamine aspartate monohydrate, dextroamphetamine sulfate and amphetamine sulfate extended-release capsules, which was attributed to the higher dose administered to children on a mg/kg body weight basis compared to adults. Upon dose normalization on a mg/kg basis, children showed 30% less systemic exposure compared to adults.
Gender
Systemic exposure to amphetamine was 20-30% higher in women (N=20) than in men (N=20) due to the higher dose administered to women on a mg/kg body weight basis. When the exposure parameters (Cmax and AUC) were normalized by dose (mg/kg), these differences diminished. Age and gender had no direct effect on the pharmacokinetics of d- and l-amphetamine.
Race
Formal pharmacokinetic studies for race have not been conducted. However, amphetamine pharmacokinetics appeared to be comparable among Caucasians (N=33), Blacks (N=8) and Hispanics (N=10).
Patients with Renal Impairment
The effect of renal impairment on d- and l- amphetamine after administration of dextroamphetamine saccharate, amphetamine aspartate monohydrate, dextroamphetamine sulfate and amphetamine sulfate extended-release capsules has not been studied. The impact of renal impairment on the disposition of amphetamine is expected to be similar between oral administration of lisdexamfetamine and dextroamphetamine saccharate, amphetamine aspartate monohydrate, dextroamphetamine sulfate and amphetamine sulfate extended-release capsules.
In a pharmacokinetic study of lisdexamfetamine in adult subjects with normal and impaired renal function, mean d-amphetamine clearance was reduced from 0.7 L/hr/kg in normal subjects to 0.4 L/hr/kg in subjects with severe renal impairment (GFR 15 to < 30 mL/min/1.73m^2). Dialysis did not significantly affect the clearance of d-amphetamine [see Use in Specific Populations (8.6)].

13 NONCLINICAL TOXICOLOGY

13.1 Carcinogenesis, Mutagenesis, Impairment of Fertility

Carcinogenesis

No evidence of carcinogenicity was found in studies in which d,l-amphetamine (enantiomer ratio of 1:1) was administered to mice and rats in the diet for 2 years at doses of up to 30 mg/kg/day in male mice, 19 mg/kg/day in female mice, and 5 mg/kg/day in male and female rats. These doses are approximately 2.4, 1.5, and 0.8 times, respectively, the maximum recommended human dose of 30 mg/day given to children, on a mg/m^2 basis.

Mutagenesis

Amphetamine, in the enantiomer ratio d- to l- ratio of 3:1, was not clastogenic in the mouse bone marrow micronucleus test in vivo and was negative when tested in the E. coli component of the Ames test in vitro. d,l-Amphetamine (1:1 enantiomer ratio) has been reported to produce a positive response in the mouse bone marrow micronucleus test, an equivocal response in the Ames test, and negative responses in the in vitro sister chromatid exchange and chromosomal aberration assays.

Impairment of Fertility

Amphetamine, in the enantiomer ratio d- to l- ratio of 3:1, did not adversely affect fertility or early embryonic development in the rat at doses of up to 20 mg/kg/day (approximately 8 times the maximum recommended human dose of 20 mg/day given to adolescents, on a mg/m^2 basis).

13.2 Animal Toxicology and/or Pharmacology

Acute administration of high doses of amphetamine (d- or d,l-) has been shown to produce long-lasting neurotoxic effects, including irreversible nerve fiber damage, in rodents. The significance of these findings to humans is unknown.

14 CLINICAL STUDIES

Pediatric Patients
A double-blind, randomized, placebo-controlled, parallel-group study was conducted in children aged 6-12 (N=584) who met DSM-IV® criteria for ADHD (either the combined type or the hyperactive- impulsive type). Patients were randomized to fixed-dose treatment groups receiving final doses of 10, 20, or 30 mg of dextroamphetamine saccharate, amphetamine aspartate monohydrate, dextroamphetamine sulfate and amphetamine sulfate extended-release capsules or placebo once daily in the morning for three weeks. Significant improvements in patient behavior, based upon teacher ratings of attention and hyperactivity, were observed for all dextroamphetamine saccharate, amphetamine aspartate monohydrate, dextroamphetamine sulfate and amphetamine sulfate extended-release capsules doses compared to patients who received placebo, for all three weeks, including the first week of treatment, when all dextroamphetamine saccharate, amphetamine aspartate monohydrate, dextroamphetamine sulfate and amphetamine sulfate extended-release capsules subjects were receiving a dose of 10 mg/day. Patients who received dextroamphetamine saccharate, amphetamine aspartate monohydrate, dextroamphetamine sulfate and amphetamine sulfate extended-release capsules showed behavioral improvements in both morning and afternoon assessments compared to patients on placebo.
In a classroom analogue study, patients (N=51) receiving fixed doses of 10 mg, 20 mg or 30 mg dextroamphetamine saccharate, amphetamine aspartate monohydrate, dextroamphetamine sulfate and amphetamine sulfate extended-release capsules demonstrated statistically significant improvements in teacher-rated behavior and performance measures, compared to patients treated with placebo.

A double-blind, randomized, multi-center, parallel-group, placebo-controlled study was conducted in adolescents aged 13-17 (N=327) who met DSM-IV® criteria for ADHD. The primary cohort of patients (n=287, weighing ≤ 75kg/165lbs) was randomized to fixed-dose treatment groups and received four weeks of treatment. Patients were randomized to receive final doses of 10 mg, 20 mg, 30 mg, and 40 mg dextroamphetamine saccharate, amphetamine aspartate monohydrate, dextroamphetamine sulfate and amphetamine sulfate extended-release capsules or placebo once daily in the morning. Patients randomized to doses greater than 10 mg were titrated to their final doses by 10 mg each week. The secondary cohort consisted of 40 subjects weighing >75kg/165lbs who were randomized to fixed-dose treatment groups receiving final doses of 50 mg and 60 mg dextroamphetamine saccharate, amphetamine aspartate monohydrate, dextroamphetamine sulfate and amphetamine sulfate extended-release capsules or placebo once daily in the morning for 4 weeks. The primary efficacy variable was the Attention Deficit Hyperactivity Disorder-Rating Scale IV (ADHD-RS-IV) total score for the primary cohort. The ADHD-RS-IV is an 18-item scale that measures the core symptoms of ADHD. Improvements in the primary cohort were statistically significantly greater in all four primary cohort active treatment groups (dextroamphetamine saccharate, amphetamine aspartate monohydrate, dextroamphetamine sulfate and amphetamine sulfate extended-release capsules 10 mg, 20 mg, 30 mg, and 40 mg) compared with the placebo group. There was not adequate evidence that doses greater than 20 mg/day conferred additional benefit.
Adult Patients
A double-blind, randomized, placebo-controlled, parallel-group study was conducted in adults (N=255) who met DSM-IV® criteria for ADHD. Patients were randomized to fixed-dose treatment groups receiving final doses of 20, 40, or 60 mg of dextroamphetamine saccharate, amphetamine aspartate monohydrate, dextroamphetamine sulfate and amphetamine sulfate extended-release capsules or placebo once daily in the morning for four weeks. Significant improvements, measured with the Attention Deficit Hyperactivity Disorder-Rating Scale (ADHD-RS), an 18-item scale that measures the core symptoms of ADHD, were observed at endpoint for all dextroamphetamine saccharate, amphetamine aspartate monohydrate, dextroamphetamine sulfate and amphetamine sulfate extended-release capsules doses compared to patients who received placebo for all four weeks. There was not adequate evidence that doses greater than 20 mg/day conferred additional benefit.

16 HOW SUPPLIED/STORAGE AND HANDLING

Dextroamphetamine saccharate, amphetamine aspartate monohydrate, dextroamphetamine sulfate and amphetamine sulfate extended-release capsules 5 mg: capsule with white opaque body and lime green cap (imprinted 5 mg on body and ELI-510 on cap with black ink). Capsules filled with orange pellets, bottles of 100, NDC 0527-5510-37
Dextroamphetamine saccharate, amphetamine aspartate monohydrate, dextroamphetamine sulfate and amphetamine sulfate extended-release capsules 10 mg: capsules with blue body and blue cap (imprinted 10 mg on body and ELI-511 on cap with black ink). Capsules filled with orange pellets, bottles of 100, NDC 0527-5511-37
Dextroamphetamine saccharate, amphetamine aspartate monohydrate, dextroamphetamine sulfate and amphetamine sulfate extended-release capsules 15 mg: capsule with white opaque body and green cap (imprinted 15 mg on body and ELI-512 on cap with black ink). Capsules filled with orange pellets, bottles of 100, NDC 0527-5512-37
Dextroamphetamine saccharate, amphetamine aspartate monohydrate, dextroamphetamine sulfate and amphetamine sulfate extended-release capsules 20 mg: capsule with white opaque body and light pink cap (imprinted 20 mg on body and ELI-513 on cap with black ink). Capsules filled with orange pellets, bottles of 100, NDC 0527-5513-37
Dextroamphetamine saccharate, amphetamine aspartate monohydrate, dextroamphetamine sulfate and amphetamine sulfate extended-release capsules 25 mg: capsules with pink body and pink cap (imprinted 25 mg on body and ELI-514 on cap with black ink). Capsules filled with orange pellets, bottles of 100, NDC 0527-5514-37
Dextroamphetamine saccharate, amphetamine aspartate monohydrate, dextroamphetamine sulfate and amphetamine sulfate extended-release capsules 30 mg: capsules with white opaque body and dark pink cap (imprinted 30 mg on body and ELI-515 on cap with black ink). Capsules filled with orange pellets, bottles of 100, NDC 0527-5515-37

STORAGE AND HANDLING

Dispense in a tight, light-resistant container as defined in the USP, with a child-resistant closure, as required.

Store at room temperature, 20° to 25° C (68° to 77° F). Excursions permitted to 15° to 30° C (59° to 86° F) [see USP CONTROLLED ROOM TEMPERATURE].

Disposal

Comply with local laws and regulations on drug disposal of CNS stimulants. Dispose of remaining, unused, or expired dextroamphetamine saccharate, amphetamine aspartate monohydrate, dextroamphetamine sulfate and amphetamine sulfate extended-release capsules at authorized collection sites such as retail pharmacies, hospital or clinic pharmacies, and law enforcement locations. If no take-back program or authorized collector is available, mix dextroamphetamine saccharate, amphetamine aspartate monohydrate, dextroamphetamine sulfate and amphetamine sulfate extended-release capsules with an undesirable, nontoxic substance to make it less appealing to children and pets. Place the mixture in a container such as a sealed plastic bag and discard dextroamphetamine saccharate, amphetamine aspartate monohydrate, dextroamphetamine sulfate and amphetamine sulfate extended-release capsules in the household trash.

17 PATIENT COUNSELING INFORMATION

Advise the patient to read the FDA-approved patient labeling (Medication Guide)
Controlled Substance Status/Potential for Abuse, Misuse, and Dependence
Advise patients that dextroamphetamine saccharate, amphetamine aspartate monohydrate, dextroamphetamine sulfate and amphetamine sulfate extended-release capsules are a federally controlled substance because it can be abused or lead to dependence. Additionally, emphasize that dextroamphetamine saccharate, amphetamine aspartate monohydrate, dextroamphetamine sulfate and amphetamine sulfate extended-release capsules should be stored in a safe place to prevent misuse and/or abuse. Evaluate patient history (including family history) of abuse or dependence on alcohol, prescription medicines, or illicit drugs [see Warnings and Precautions (5.1), Drug Abuse and Dependence (9)].
Serious Cardiovascular Risks
Advise patients of serious cardiovascular risk (including sudden death, myocardial infarction, stroke, and hypertension) with dextroamphetamine saccharate, amphetamine aspartate monohydrate, dextroamphetamine sulfate and amphetamine sulfate extended-release capsules. Patients who develop symptoms such as exertional chest pain, unexplained syncope, or other symptoms suggestive of cardiac disease during treatment should undergo a prompt cardiac evaluation [see Warnings and Precautions (5.1)].
Psychiatric Risks
Prior to initiating treatment with dextroamphetamine saccharate, amphetamine aspartate monohydrate, dextroamphetamine sulfate and amphetamine sulfate extended-release capsules, adequately screen patients with comorbid depressive symptoms to determine if they are at risk for bipolar disorder. Such screening should include a detailed psychiatric history, including a family history of suicide, bipolar disorder, and/or depression. Additionally, dextroamphetamine saccharate, amphetamine aspartate monohydrate, dextroamphetamine sulfate and amphetamine sulfate extended-release capsules therapy at usual doses may cause treatment-emergent psychotic or manic symptoms in patients without prior history of psychotic symptoms or mania [see Warnings and Precautions (5.2)].
Circulation problems in fingers and toes [Peripheral vasculopathy, including Raynaud's phenomenon]
Instruct patients beginning treatment with dextroamphetamine saccharate, amphetamine aspartate monohydrate, dextroamphetamine sulfate and amphetamine sulfate extended-release capsules about the risk of peripheral vasculopathy, including Raynaud's Phenomenon, and in associated signs and symptoms: fingers or toes may feel numb, cool, painful, and/or may change color from pale, to blue, to red. Instruct patients to report to their physician any new numbness, pain, skin color change, or sensitivity to temperature in fingers or toes. Instruct patients to call their physician immediately with any signs of unexplained wounds appearing on fingers or toes while taking dextroamphetamine saccharate, amphetamine aspartate monohydrate, dextroamphetamine sulfate and amphetamine sulfate extended-release capsules. Further clinical evaluation (e.g., rheumatology referral) may be appropriate for certain patients [see Warnings and Precautions (5.5)].
Serotonin Syndrome
Caution patients about the risk of serotonin syndrome with concomitant use of dextroamphetamine saccharate, amphetamine aspartate monohydrate, dextroamphetamine sulfate and amphetamine sulfate extended-release capsules and other serotonergic drugs including SSRIs, SNRIs, triptans, tricyclic antidepressants, fentanyl, lithium, tramadol, tryptophan, buspirone, St. John's Wort, and with drugs that impair metabolism of serotonin (in particular MAOIs, both those intended to treat psychiatric disorders and also others such as linezolid [see Contraindications (4), Warnings and Precautions (5.6) and Drug Interactions (7.1)]. Advise patients to contact their healthcare provider or report to the emergency room if they experience signs or symptoms of serotonin syndrome.
Concomitant Medications
Advise patients to notify their physicians if they are taking, or plan to take, any prescription or over-the-counter drugs because there is a potential for interactions [see Drug Interactions (7.1)].
Growth
Monitor growth in children during treatment with dextroamphetamine saccharate, amphetamine aspartate monohydrate, dextroamphetamine sulfate and amphetamine sulfate extended-release capsules, and patients who are not growing or gaining weight as expected may need to have their treatment interrupted [see Warnings and Precautions (5.3)].
Pregnancy Registry
Advise patients that there is a pregnancy exposure registry that monitors pregnancy outcomes in women exposed to dextroamphetamine saccharate, amphetamine aspartate monohydrate, dextroamphetamine sulfate and amphetamine sulfate extended-release capsules during pregnancy [see Use in Specific Populations (8.1)].
Pregnancy
Advise patients to notify their healthcare provider if they become pregnant or intend to become pregnant during treatment with amphetamine aspartate monohydrate, dextroamphetamine sulfate and amphetamine sulfate extended-release capsules. Advise patients of the potential fetal effects from the use of amphetamine aspartate monohydrate, dextroamphetamine sulfate and amphetamine sulfate extended-release capsules during pregnancy [see Use in Specific Populations (8.1)].
Lactation
Advise women not to breastfeed if they are taking dextroamphetamine saccharate, amphetamine aspartate monohydrate, dextroamphetamine sulfate and amphetamine sulfate extended-release capsules [see Use in Specific Populations (8.2)].
Impairment in Ability to Operate Machinery or Vehicles
Dextroamphetamine saccharate, amphetamine aspartate monohydrate, dextroamphetamine sulfate and amphetamine sulfate extended-release capsules may impair the ability of the patient to engage in potentially hazardous activities such as operating machinery or vehicles; the patient should therefore be cautioned accordingly.
Distributed by:
Lannett Company, Inc.
Philadelphia, PA 19136
For more information call 1-844-834-0530
IN0536
Rev. 12/2019

MEDICATION GUIDE

DEXTROAMPHETAMINE SACCHARATE, AMPHETAMINE ASPARTATE MONOHYDRATE, DEXTROAMPHETAMINE SULFATE AND AMPHETAMINE SULFATE EXTENDED-RELEASE CAPSULES
(DEX-troe-am-FET-uh-meen SACK-uh-rate, am-FET-uh-meen ass-PAR-tate, MAN-no-HIGH-drate, DEX-troe-am-FET-uh-meen SULL-fate, and am-FET-uh-meen SULL-fate), CII
Read the Medication Guide that comes with dextroamphetamine saccharate, amphetamine aspartate monohydrate, dextroamphetamine sulfate and amphetamine sulfate extended-release capsules before you or your child starts taking it and each time you get a refill. There may be new information. This Medication Guide does not take the place of talking to your doctor about you or your child's treatment with dextroamphetamine saccharate, amphetamine aspartate monohydrate, dextroamphetamine sulfate and amphetamine sulfate extended-release capsules.
What is the most important information I should know about dextroamphetamine saccharate, amphetamine aspartate monohydrate, dextroamphetamine sulfate and amphetamine sulfate extended-release capsules?
Dextroamphetamine saccharate, amphetamine aspartate monohydrate, dextroamphetamine sulfate and amphetamine sulfate extended-release capsules is a stimulant medicine. The following have been reported with use of stimulant medicines.
1. Heart-related problems:

Tell your doctor if you or your child have any heart problems, heart defects, high blood pressure, or a family history of these problems.
Your doctor should check you or your child carefully for heart problems before starting dextroamphetamine saccharate, amphetamine aspartate monohydrate, dextroamphetamine sulfate and amphetamine sulfate extended-release capsules.
Your doctor should check you or your child's blood pressure and heart rate regularly during treatment with dextroamphetamine saccharate, amphetamine aspartate monohydrate, dextroamphetamine sulfate and amphetamine sulfate extended-release capsules.
Call your doctor right away if you or your child has any signs of heart problems such as chest pain, shortness of breath, or fainting while taking dextroamphetamine saccharate, amphetamine aspartate monohydrate, dextroamphetamine sulfate and amphetamine sulfate extended-release capsules.
2. Mental (Psychiatric) problems:
All Patients

- new or worse behavior and thought problems
- new or worse bipolar illness
- new or worse aggressive behavior or hostility

Children and Teenagers

- new psychotic symptoms (such as hearing voices, believing things that are not true, are suspicious) or new manic symptoms

Tell your doctor about any mental problems you or your child have, or about a family history of suicide, bipolar illness, or depression.
Call your doctor right away if you or your child have any new or worsening mental symptoms or problems while taking dextroamphetamine saccharate, amphetamine aspartate monohydrate, dextroamphetamine sulfate and amphetamine sulfate extended-release capsules, especially seeing or hearing things that are not real, believing things that are not real, or are suspicious.
3. Circulation problems in fingers and toes [Peripheral vasculopathy, including Raynaud's phenomenon]:

- Fingers or toes may feel numb, cool, painful
- Fingers or toes may change from pale, to blue, to red

Tell your doctor if you have or your child has numbness, pain, skin color change, or sensitivity to temperature in your fingers or toes.
Call your doctor right away if you have or your child has any unexplained wounds appearing on fingers or toes while taking dextroamphetamine saccharate, amphetamine aspartate monohydrate, dextroamphetamine sulfate and amphetamine sulfate extended-release capsules.
What is dextroamphetamine saccharate, amphetamine aspartate monohydrate, dextroamphetamine sulfate and amphetamine sulfate extended-release capsules?
Dextroamphetamine saccharate, amphetamine aspartate monohydrate, dextroamphetamine sulfate and amphetamine sulfate extended-release capsules is a once daily central nervous system stimulant prescription medicine. It is used for the treatment of Attention Deficit Hyperactivity Disorder (ADHD). Dextroamphetamine saccharate, amphetamine aspartate monohydrate, dextroamphetamine sulfate and amphetamine sulfate extended-release capsules may help increase attention and decrease impulsiveness and hyperactivity in patients with ADHD.
Dextroamphetamine saccharate, amphetamine aspartate monohydrate, dextroamphetamine sulfate and amphetamine sulfate extended-release capsules should be used as a part of a total treatment program for ADHD that may include counseling or other therapies.
Dextroamphetamine saccharate, amphetamine aspartate monohydrate, dextroamphetamine sulfate and amphetamine sulfate extended-release capsules is a federally controlled substance (CII) because it can be abused or lead to dependence. Keep dextroamphetamine saccharate, amphetamine aspartate monohydrate, dextroamphetamine sulfate and amphetamine sulfate extended-release capsules in a safe place to prevent misuse and abuse. Selling or giving away dextroamphetamine saccharate, amphetamine aspartate monohydrate, dextroamphetamine sulfate and amphetamine sulfate extended-release capsules may harm others, and is against the law.
Tell your doctor if you or your child have (or have a family history of) ever abused or been dependent on alcohol, prescription medicines or street drugs.
Who should not take dextroamphetamine saccharate, amphetamine aspartate monohydrate, dextroamphetamine sulfate and amphetamine sulfate extended-release capsules?
Dextroamphetamine saccharate, amphetamine aspartate monohydrate, dextroamphetamine sulfate and amphetamine sulfate extended-release capsulesshould not be taken if you or your child:

- have heart disease or hardening of the arteries
- have moderate to severe high blood pressure
- have hyperthyroidism
- have an eye problem called glaucoma
- are very anxious, tense, or agitated
- have a history of drug abuse
- are taking or have taken within the past 14 days an anti-depression medicine called a monoamine oxidase inhibitor or MAOI.
- is sensitive to, allergic to, or had a reaction to other stimulant medicines

Dextroamphetamine saccharate, amphetamine aspartate monohydrate, dextroamphetamine sulfate and amphetamine sulfate extended-release capsules has not been studied in children less than 6 years old.
Dextroamphetamine saccharate, amphetamine aspartate monohydrate, dextroamphetamine sulfate and amphetamine sulfate extended-release capsules may not be right for you or your child. Before starting dextroamphetamine saccharate, amphetamine aspartate monohydrate, dextroamphetamine sulfate and amphetamine sulfate extended-release capsules tell you or your child's doctor about all health conditions (or a family history of) including if you or your child:

- have heart problems, heart defects, or high blood pressure
- have mental problems including psychosis, mania, bipolar illness, or depression
- have tics or Tourette's syndrome
- have liver problems
- have kidney problems
- have end stage renal disease (ESRD)
- have thyroid problems
- have seizures or have had an abnormal brain wave test (EEG)
- have circulation problems in fingers and toes
- are pregnant or plan to become pregnant. It is not known if dextroamphetamine saccharate, amphetamine aspartate monohydrate, dextroamphetamine sulfate and amphetamine sulfate extended-release capsules will harm your unborn baby.
  - There is a pregnancy registry for females who are exposed to dextroamphetamine saccharate, amphetamine aspartate monohydrate, dextroamphetamine sulfate and amphetamine sulfate extended-release capsules during pregnancy. The purpose of the registry is to collect information about the health of females exposed to dextroamphetamine saccharate, amphetamine aspartate monohydrate, dextroamphetamine sulfate and amphetamine sulfate extended-release capsules and their baby. If you or your child becomes pregnant during treatment with dextroamphetamine saccharate, amphetamine aspartate monohydrate, dextroamphetamine sulfate and amphetamine sulfate extended-release capsules, talk to your healthcare provider about registering with the National Pregnancy Registry of Psychostimulants at 1-866-961-2388 or visit online at https://womensmentalhealth.org/clinical-and-researchprograms/pregnancyregistry/othermedications/.
  - are breastfeeding or plan to breastfeed. Dextroamphetamine saccharate, amphetamine aspartate monohydrate, dextroamphetamine sulfate and amphetamine sulfate passes into breast milk. You or your child should not breastfeed during treatment with dextroamphetamine saccharate, amphetamine aspartate monohydrate, dextroamphetamine sulfate and amphetamine sulfate extended-release capsules.

Can dextroamphetamine saccharate, amphetamine aspartate monohydrate, dextroamphetamine sulfate and amphetamine sulfate extended-release capsules be taken with other medicines?
Tell your doctor about all of the medicines that you or your child takes including prescription and non-prescription medicines, vitamins, and herbal supplements. Dextroamphetamine saccharate, amphetamine aspartate monohydrate, dextroamphetamine sulfate and amphetamine sulfate extended-release capsules and some medicines may interact with each other and cause serious side effects. Sometimes the doses of other medicines will need to be adjusted while taking dextroamphetamine saccharate, amphetamine aspartate monohydrate, dextroamphetamine sulfate and amphetamine sulfate extended-release capsules.
Your doctor will decide whether dextroamphetamine saccharate, amphetamine aspartate monohydrate, dextroamphetamine sulfate and amphetamine sulfate extended-release capsules can be taken with other medicines.
Especially tell your doctor if you or your child takes:

- anti-depression medicines including MAOIs
- anti-psychotic medicines
- lithium
- narcotic pain medicines
- seizure medicines
- blood thinner medicines
- blood pressure medicines
- stomach acid medicines
- cold or allergy medicines that contain decongestants

Know the medicines that you or your child takes. Keep a list of your medicines with you to show your doctor and pharmacist.
Do not start any new medicine while taking dextroamphetamine saccharate, amphetamine aspartate monohydrate, dextroamphetamine sulfate and amphetamine sulfate extended-release capsules without talking to your doctor first.
How should dextroamphetamine saccharate, amphetamine aspartate monohydrate, dextroamphetamine sulfate and amphetamine sulfate extended-release capsules be taken?

- Take dextroamphetamine saccharate, amphetamine aspartate monohydrate, dextroamphetamine sulfate and amphetamine sulfate extended-release capsules exactly as prescribed. Your doctor may adjust the dose until it is right for you or your child.
- Take dextroamphetamine saccharate, amphetamine aspartate monohydrate, dextroamphetamine sulfate and amphetamine sulfate extended-release capsules once a day in the morning when you first wake up. Dextroamphetamine saccharate, amphetamine aspartate monohydrate, dextroamphetamine sulfate and amphetamine sulfate extended-release capsules is an extended release capsule. It releases medicine into your body throughout the day.
- Swallow dextroamphetamine saccharate, amphetamine aspartate monohydrate, dextroamphetamine sulfate and amphetamine sulfate extended-release capsules whole with water or other liquids. If you or your child cannot swallow the capsule, open it and sprinkle the medicine over a spoonful of applesauce. Swallow all of the applesauce and medicine mixture without chewing immediately. Follow with a drink of water or other liquid. Never chew or crush the capsule or the medicine inside the capsule.
- Dextroamphetamine saccharate, amphetamine aspartate monohydrate, dextroamphetamine sulfate and amphetamine sulfate extended-release capsules can be taken with or without food.
- From time to time, your doctor may stop dextroamphetamine saccharate, amphetamine aspartate monohydrate, dextroamphetamine sulfate and amphetamine sulfate extended-release capsules treatment for a while to check ADHD symptoms.
- Your doctor may do regular checks of the heart and blood pressure while taking dextroamphetamine saccharate, amphetamine aspartate monohydrate, dextroamphetamine sulfate and amphetamine sulfate extended-release capsules. Children should have their height and weight checked often while taking dextroamphetamine saccharate, amphetamine aspartate monohydrate, dextroamphetamine sulfate and amphetamine sulfate extended-release capsules. Dextroamphetamine saccharate, amphetamine aspartate monohydrate, dextroamphetamine sulfate and amphetamine sulfate extended-release capsules treatment may be stopped if a problem is found during these check-ups.
- If you or your child takes too much dextroamphetamine saccharate, amphetamine aspartate monohydrate, dextroamphetamine sulfate and amphetamine sulfate extended-release capsules or overdoses, call your doctor or poison control center right away, or get emergency treatment.

What are possible side effects of dextroamphetamine saccharate, amphetamine aspartate monohydrate, dextroamphetamine sulfate and amphetamine sulfate extended-release capsules?
See "What is the most important information I should know about dextroamphetamine saccharate, amphetamine aspartate monohydrate, dextroamphetamine sulfate and amphetamine sulfate extended-release capsules?" for information on reported heart and mental problems.
Other serious side effects include:

- slowing of growth (height and weight) in children
- seizures, mainly in patients with a history of seizures
- eyesight changes or blurred vision

Common side effects include:

- headache
- decreased appetite
- stomach ache
- nervousness
- trouble sleeping
- mood swings
- weight loss
- dizziness
- dry mouth
- fast heart beat

Dextroamphetamine saccharate, amphetamine aspartate monohydrate, dextroamphetamine sulfate and amphetamine sulfate extended-release capsules may affect you or your child's ability to drive or do other dangerous activities.
Talk to your doctor if you or your child has side effects that are bothersome or do not go away.
This is not a complete list of possible side effects. Ask your doctor or pharmacist for more information.
Call your doctor for medical advice about side effects. You may report side effects to FDA at 1-800- FDA-1088.
How should I store dextroamphetamine saccharate, amphetamine aspartate monohydrate, dextroamphetamine sulfate and amphetamine sulfate extended-release capsules?

- Store dextroamphetamine saccharate, amphetamine aspartate monohydrate, dextroamphetamine sulfate and amphetamine sulfate extended-release capsules in a safe place at room temperature, 59° to 86° F (15° to 30° C).
- Keep dextroamphetamine saccharate, amphetamine aspartate monohydrate, dextroamphetamine sulfate and amphetamine sulfate extended-release capsules and all medicines out of the reach of children.

General information about dextroamphetamine saccharate, amphetamine aspartate monohydrate, dextroamphetamine sulfate and amphetamine sulfate extended-release capsules
Medicines are sometimes prescribed for purposes other than those listed in a Medication Guide. Do not use dextroamphetamine saccharate, amphetamine aspartate monohydrate, dextroamphetamine sulfate and amphetamine sulfate extended-release capsules for a condition for which it was not prescribed. Do not give dextroamphetamine saccharate, amphetamine aspartate monohydrate, dextroamphetamine sulfate and amphetamine sulfate extended-release capsules to other people, even if they have the same condition. It may harm them and it is against the law.
This Medication Guide summarizes the most important information about dextroamphetamine saccharate, amphetamine aspartate monohydrate, dextroamphetamine sulfate and amphetamine sulfate extended-release capsules. If you would like more information, talk with your doctor. You can ask your doctor or pharmacist for information about dextroamphetamine saccharate, amphetamine aspartate monohydrate, dextroamphetamine sulfate and amphetamine sulfate extended-release capsules that was written for healthcare professionals. For more information, you may also contact Lannett Company, Inc. at 1-844-834-0530 or FDA at 1-800-FDA-1088 or www.fda.gov/medwatch.
What are the ingredients in dextroamphetamine saccharate, amphetamine aspartate monohydrate, dextroamphetamine sulfate and amphetamine sulfate extended-release capsules?
Active Ingredients: dextroamphetamine saccharate, amphetamine aspartate monohydrate, dextroamphetamine sulfate USP, amphetamine sulfate USP
Inactive Ingredients: ferric oxide red, ferric oxide yellow, gelatin capsules, hypromellose 2910/3 cP, 6 cP and 50 cP, methacrylic acid and ethyl acrylate copolymer, titanium dioxide, polyethylene glycol, polysorbate 80, sugar spheres, talc, and triethyl citrate.
The 5 mg gelatin capsules contain gelatin, titanium dioxide, D&C yellow #10, FD&C blue #1 and FD&C yellow #6.
The 10 mg gelatin capsules contain gelatin, FD&C blue #1, and FD&C red #40.
The 15 mg gelatin capsules contain gelatin, titanium dioxide, FD&C blue #1, and FD&C yellow #6.
The 20 mg gelatin capsules contain gelatin, titanium dioxide, and FD&C red #3.
The 25 mg gelatin capsules contain gelatin, FD&C red #40, and FD&C yellow #6.
The 30 mg gelatin capsules contain gelatin, titanium dioxide, D&C red #28, and FD&C red #40.
The ink ingredients are common for all strengths: the capsule imprint black ink contains FD&C blue #1 aluminum lake, FD&C red #40 aluminum lake, FD&C yellow #6 aluminum lake, propylene glycol, and shellac.
Distributed by:
Lannett Company, Inc.
Philadelphia, PA 19136
For more information call 1-844-834-0530
This Medication Guide has been approved by the U.S. Food and Drug Administration.
PI0016
Revised: 12/2019

PACKAGE LABEL.PRINCIPAL DISPLAY PANEL

Dextroamphetamine Saccharate, Amphetamine Aspartate Monohydrate, Dextroamphetamine Sulfate, and Amphetamine Sulfate

(Mixed Salts of A Single-Entity
Amphetamine Product)

Extended-Release Capsules

NDC 0527-5510-37
5 mg

CII
100 Capsules

Rx only

Dextroamphetamine Saccharate, Amphetamine Aspartate Monohydrate, Dextroamphetamine Sulfate, and Amphetamine Sulfate

(Mixed Salts of A Single-Entity
Amphetamine Product)

Extended-Release Capsules

NDC 0527-5511-37
10 mg

CII
100 Capsules

Rx only

Dextroamphetamine Saccharate, Amphetamine Aspartate Monohydrate, Dextroamphetamine Sulfate, and Amphetamine Sulfate

(Mixed Salts of A Single-Entity
Amphetamine Product)

Extended-Release Capsules

NDC 0527-5512-37
15 mg

CII
100 Capsules

Rx only

Dextroamphetamine Saccharate, Amphetamine Aspartate Monohydrate, Dextroamphetamine Sulfate, and Amphetamine Sulfate

(Mixed Salts of A Single-Entity
Amphetamine Product)

Extended-Release Capsules

NDC 0527-5513-37
20 mg

CII
100 Capsules

Rx only

Dextroamphetamine Saccharate, Amphetamine Aspartate Monohydrate, Dextroamphetamine Sulfate, and Amphetamine Sulfate

(Mixed Salts of A Single-Entity
Amphetamine Product)

Extended-Release Capsules

NDC 0527-5514-37
25 mg

CII
100 Capsules

Rx only

Dextroamphetamine Saccharate, Amphetamine Aspartate Monohydrate, Dextroamphetamine Sulfate, and Amphetamine Sulfate

(Mixed Salts of A Single-Entity
Amphetamine Product)

Extended-Release Capsules

NDC 0527-5515-37
30 mg

CII
100 Capsules

Rx only